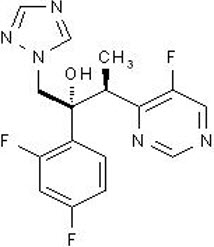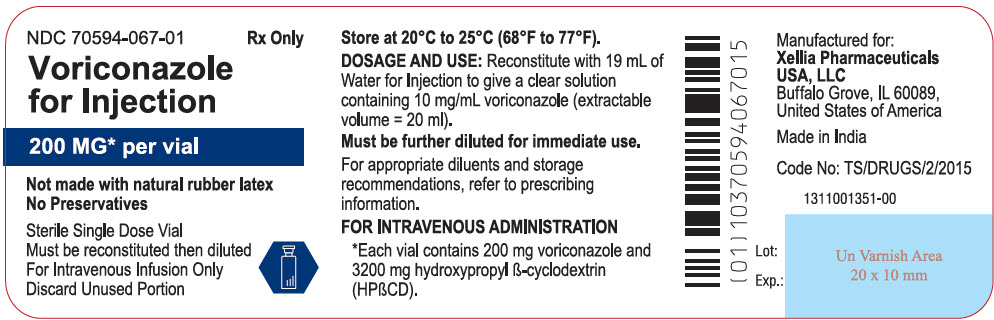 DRUG LABEL: Voriconazole
NDC: 70594-067 | Form: INJECTION, POWDER, LYOPHILIZED, FOR SOLUTION
Manufacturer: Xellia Pharmaceuticals USA LLC
Category: prescription | Type: HUMAN PRESCRIPTION DRUG LABEL
Date: 20230111

ACTIVE INGREDIENTS: VORICONAZOLE 10 mg/1 mL
INACTIVE INGREDIENTS: HYDROXYPROPYL BETADEX

HIGHLIGHTS OF PRESCRIBING INFORMATION

These highlights do not include all the information needed to use VORICONAZOLE for injection safely and effectively. See full prescribing information for VORICONAZOLE for injection.
VORICONAZOLE for injection, for intravenous use
Initial U.S. Approval: 2002

RECENT MAJOR CHANGES

Contraindications (4) | 1/2023
Warnings and Precautions, Photosensitivity (5.6) | 1/2023

1 INDICATIONS AND USAGE

Voriconazole for injection is an azole antifungal indicated for use in the treatment of adults and pediatric patients aged 12 to 14 years weighing greater than or equal to 50 kg and those aged 15 years and older regardless of body weight with:

- Invasive aspergillosis (1.1)
- Candidemia in non-neutropenics and other deep tissue Candida infections (1.2)
- Serious fungal infections caused by Scedosporium apiospermum and Fusarium species including Fusarium solani, in patients intolerant of, or refractory to, other therapy (1.3)

2 DOSAGE AND ADMINISTRATION

- Dosage in Adults (2.3)
  Infection | Loading dose | Maintenance Dose
  Infection | Intravenous infusion | Intravenous infusion
  Invasive Aspergillosis | 6 mg/kg every 12 hours for the first 24 hours | 4 mg/kg every 12 hours
  Candidemia in nonneutropenics and other deep tissue Candida infections | 6 mg/kg every 12 hours for the first 24 hours | 3–4 mg/kg every 12 hours
  Scedosporiosis and Fusariosis | 6 mg/kg every 12 hours for the first 24 hours | 4 mg/kg every 12 hours
- Hepatic Impairment: Use half the maintenance dose in adult patients with mild to moderate hepatic impairment (Child-Pugh Class A and B) (2.5)
- Renal Impairment: Avoid intravenous administration in adult patients with moderate to severe renal impairment (creatinine clearance <50 mL/min) (2.6)

- Dosage in Pediatric Patients (2.4)
- For pediatric patients aged 12 to 14 years weighing greater than or equal to 50 kg and those aged 15 years and older regardless of body weight use adult dosage. (2.4)
- Dosage adjustment of Voriconazole for injection in pediatric patients with renal or hepatic impairment has not been established. (2.5, 2.6)
- See full prescribing information for instructions on reconstitution of Voriconazole for injection lyophilized powder for intravenous use (2.8)

3 DOSAGE FORMS AND STRENGTHS

For Injection: Lyophilized white to off white cake or powder containing 200 mg voriconazole and 3,200 mg of hydroxypropyl β-cyclodextrin (HPβCD); after reconstitution 10 mg/mL of voriconazole and 160 mg/mL of HPβCD (3)

4 CONTRAINDICATIONS

- Hypersensitivity to voriconazole or its excipients (4)
- Coadministration with pimozide, quinidine, sirolimus or ivabradine due to risk of serious adverse reactions (4, 7)
- Coadministration with rifampin, carbamazepine, long-acting barbiturates, efavirenz, ritonavir, rifabutin, ergot alkaloids, and St. John's Wort due to risk of loss of efficacy (4, 7)
- Coadministration with naloxegol, tolvaptan, and lurasidone due to risk of adverse reactions (4, 7)
- Coadministration of Voriconazole for injection with venetoclax at initiation and during the ramp-up phase in patients with chronic lymphocytic leukemia (CLL) or small lymphocytic lymphoma (SLL) due to increased risk of adverse reactions (4, 7)

5 WARNINGS AND PRECAUTIONS

- Hepatic Toxicity: Serious hepatic reactions reported. Evaluate liver function tests at start of and during Voriconazole for injection therapy (5.1)
- Arrhythmias and QT Prolongation: Correct potassium, magnesium and calcium prior to use; caution patients with proarrhythmic conditions (5.2)
- Infusion Related Reactions (including anaphylaxis): Stop the infusion (5.3)
- Visual Disturbances (including optic neuritis and papilledema): Monitor visual function if treatment continues beyond 28 days (5.4)
- Severe Cutaneous Adverse Reactions: Discontinue for exfoliative cutaneous reactions (5.5)
- Photosensitivity: Avoid sunlight due to risk of photosensitivity (5.6)
- Adrenal Dysfunction: Carefully monitor patients receiving Voriconazole for injection and corticosteroids (via all routes of administration) for adrenal dysfunction both during and after Voriconazole for injection treatment. Instruct patients to seek immediate medical care if they develop signs and symptoms of Cushing's syndrome or adrenal insufficiency (5.8)
- Embryo-Fetal Toxicity: Voriconazole can cause fetal harm when administered to a pregnant woman. Inform pregnant patients of the potential hazard to the fetus. Advise females of reproductive potential to use effective contraception during treatment with Voriconazole for injection (5.9, 8.1, 8.3)
- Skeletal Adverse Reactions: Fluorosis and periostitis with long-term voriconazole therapy. Discontinue if these adverse reactions occur (5.12)
- Clinically Significant Drug Interactions: Review patient's concomitant medications (5.13, 7)

6 ADVERSE REACTIONS

- Adult patients: The most common adverse reactions (incidence ≥2%): were visual disturbances, fever, nausea, rash, vomiting, chills, headache, liver function test abnormal, tachycardia, hallucinations (6)

To report SUSPECTED ADVERSE REACTIONS, contact Xellia Pharmaceuticals USA, LLC at 1-833-295-6953, or FDA at 1-800-FDA-1088 or www.fda.gov/medwatch.

7 DRUG INTERACTIONS

- CYP3A4, CYP2C9, and CYP2C19 inhibitors and inducers: Adjust Voriconazole for injection dosage and monitor for adverse reactions or lack of efficacy (4, 7)
- Voriconazole for injection may increase the concentrations and activity of drugs that are CYP3A4, CYP2C9 and CYP2C19 substrates. Reduce dosage of these other drugs and monitor for adverse reactions (4, 7)
- Phenytoin or Efavirenz: With co-administration, increase maintenance intravenous dosage of Voriconazole for injection (2.3, 2.7, 7)

8 USE IN SPECIFIC POPULATIONS

- Pediatrics: Safety and effectiveness in patients younger than 2 years has not been established (8.4)

Additional pediatric use information is approved for PF PRISM C.V.'s VFEND (voriconazole) for injection. However, due to PF PRISM C.V.'s marketing exclusivity rights, this drug product is not labeled with that information.

FULL PRESCRIBING INFORMATION

1 INDICATIONS AND USAGE

1.1 Invasive Aspergillosis

Voriconazole for injection is indicated in adults and pediatric patients (aged 12 to 14 years weighing greater than or equal to 50 kg and those aged 15 years and older regardless of body weight) for the treatment of invasive aspergillosis (IA). In clinical trials, the majority of isolates recovered were Aspergillus fumigatus. There was a small number of cases of culture-proven disease due to species of Aspergillus other than A. fumigatus [see Clinical Studies (14.1) and Microbiology (12.4)].

1.2 Candidemia in Non-neutropenic Patients and Other Deep Tissue Candida Infections

Voriconazole for injection is indicated in adult and pediatric patients (aged 12 to 14 years weighing greater than or equal to 50 kg and those aged 15 years and older regardless of body weight) for the treatment of candidemia in non-neutropenic patients and the following Candida infections: disseminated infections in skin and infections in abdomen, kidney, bladder wall, and wounds [see Clinical Studies (14.2) and Microbiology (12.4)].

1.3 Scedosporiosis and Fusariosis

Voriconazole for injection is indicated for the treatment of serious fungal infections caused by Scedosporium apiospermum (asexual form of Pseudallescheria boydii) and Fusarium spp. including Fusarium solani, in adult and pediatric patients (aged 12 to 14 years weighing greater than or equal to 50 kg and those aged 15 years and older regardless of body weight) intolerant of, or refractory to, other therapy [see Clinical Studies (14.3) and Microbiology (12.4)].

1.4 Usage

Specimens for fungal culture and other relevant laboratory studies (including histopathology) should be obtained prior to therapy to isolate and identify causative organism(s). Therapy may be instituted before the results of the cultures and other laboratory studies are known. However, once these results become available, antifungal therapy should be adjusted accordingly.

Additional pediatric use information is approved for PF PRISM C.V.'s VFEND (voriconazole) for injection. However, due to PF PRISM C.V.'s marketing exclusivity rights, this drug product is not labeled with that information.

2 DOSAGE AND ADMINISTRATION

2.1 Important Administration Instructions for Use in All Patients

Voriconazole for injection requires reconstitution to 10 mg/mL and subsequent dilution to 5 mg/mL or less prior to administration as an infusion, at a maximum rate of 3 mg/kg per hour over 1 to 3 hours.

Administer diluted Voriconazole for injection by intravenous infusion over 1 to 3 hours only. Do not administer as an IV bolus injection.

2.2 Use of Voriconazole for injection With Other Parenteral Drug Products

Blood products and concentrated electrolytes

Voriconazole for injection must not be infused concomitantly with any blood product or short-term infusion of concentrated electrolytes, even if the two infusions are running in separate intravenous lines (or cannulas). Electrolyte disturbances such as hypokalemia, hypomagnesemia and hypocalcemia should be corrected prior to initiation of and during Voriconazole for injection therapy [see Warnings and Precautions (5.10)].

Intravenous solutions containing (non-concentrated) electrolytes

Voriconazole for injection can be infused at the same time as other intravenous solutions containing (non-concentrated) electrolytes, but must be infused through a separate line.

Total parenteral nutrition (TPN)

Voriconazole for injection can be infused at the same time as total parenteral nutrition, but must be infused in a separate line. If infused through a multiple-lumen catheter, TPN needs to be administered using a different port from the one used for Voriconazole for injection.

2.3 Recommended Dosing Regimen in Adults

Invasive aspergillosis and serious fungal infections due to Fusarium spp. and Scedosporium apiospermum

See Table 1. Therapy must be initiated with the specified loading dose regimen of intravenous Voriconazole for injection on Day 1 followed by the recommended maintenance dose (RMD) regimen. Intravenous treatment should be continued for at least 7 days. Once the patient has clinically improved and can tolerate medication given by mouth, the oral tablet form or oral suspension form of voriconazole may be utilized. The recommended oral maintenance dose of 200 mg achieves a voriconazole exposure similar to 3 mg/kg intravenously; a 300 mg oral dose achieves an exposure similar to 4 mg/kg intravenously [see Clinical Pharmacology (12.3)].

Candidemia in non-neutropenic patients and other deep tissue Candida infections

See Table 1. Patients should be treated for at least 14 days following resolution of symptoms or following last positive culture, whichever is longer.

Table 1: Recommended Dosing Regimen (Adults)
Infection | Loading Dose | Maintenance Dose [Increase dose when Voriconazole for injection is co-administered with phenytoin or efavirenz (7); Decrease dose in patients with hepatic impairment (2.5)]
 | Intravenous infusion | Intravenous infusion
Invasive Aspergillosis [In a clinical study of IA, the median duration of intravenous Voriconazole for injection therapy was 10 days (range 2 to 85 days) (14.1).] | 6 mg/kg every 12 hours for the first 24 hours | 4 mg/kg every 12 hours
Candidemia in nonneutropenic patients and other deep tissue Candida infections | 6 mg/kg every 12 hours for the first 24 hours | 3–4 mg/kg every 12 hours [In clinical trials, patients with candidemia received 3 mg/kg intravenous infusion every 12 hours as primary therapy, while patients with other deep tissue Candida infections received 4 mg/kg every 12 hours as salvage therapy. Appropriate dose should be based on the severity and nature of the infection.]
Scedosporiosis and Fusariosis | 6 mg/kg every 12 hours for the first 24 hours | 4 mg/kg every 12 hours

Method for Adjusting the Dosing Regimen in Adults

If patient is unable to tolerate 4 mg/kg intravenously every 12 hours, reduce the intravenous maintenance dose to 3 mg/kg every 12 hours.

2.4 Recommended Dosing Regimen in Pediatric Patients

For pediatric patients 12 to 14 years of age with a body weight greater than or equal to 50 kg and those 15 years of age and above regardless of body weight, administer the adult dosing regimen of Voriconazole for injection [see Dosage and Administration (2.3)].

Initiate therapy with an intravenous infusion regimen. Consider an oral regimen only after there is a significant clinical improvement.

Method for Adjusting the Dosing Regimen in Pediatric Patients

Pediatric patients 12 to 14 years of age weighing greater than or equal to 50 kg and 15 years of age and older regardless of body weight:

Use the optimal method for titrating dosage recommended for adults [see Dosage and Administration (2.3)].

Additional pediatric use information is approved for PF PRISM C.V.'s VFEND (voriconazole) for injection. However, due to PF PRISM C.V.'s marketing exclusivity rights, this drug product is not labeled with that information.

2.5 Dosage Modifications in Patients With Hepatic Impairment

Adults

The maintenance dose of Voriconazole for injection should be reduced in adult patients with mild to moderate hepatic impairment, Child-Pugh Class A and B. There are no PK data to allow for dosage adjustment recommendations in patients with severe hepatic impairment (Child-Pugh Class C).

Duration of therapy should be based on the severity of the patient's underlying disease, recovery from immunosuppression, and clinical response.

Adult patients with baseline liver function tests (ALT, AST) up to 5 times the upper limit of normal (ULN) were included in the clinical program. Dose adjustments are not necessary for adult patients with this degree of abnormal liver function, but continued monitoring of liver function tests for further elevations is recommended [see Warnings and Precautions (5.1)].

It is recommended that the recommended Voriconazole for injection loading dose regimens be used, but that the maintenance dose be halved in adult patients with mild to moderate hepatic cirrhosis (Child-Pugh Class A and B) [see Clinical Pharmacology (12.3)].

Voriconazole for injection has not been studied in adult patients with severe hepatic cirrhosis (Child-Pugh Class C) or in patients with chronic hepatitis B or chronic hepatitis C disease. Voriconazole for injection has been associated with elevations in liver function tests and clinical signs of liver damage, such as jaundice. Voriconazole for injection should only be used in patients with severe hepatic impairment if the benefit outweighs the potential risk. Patients with hepatic impairment must be carefully monitored for drug toxicity.

Pediatric Patients

Dosage adjustment of Voriconazole for injection in pediatric patients with hepatic impairment has not been established [see Use in Specific Populations (8.4)].

2.6 Dosage Modifications in Patients With Renal Impairment

Adult Patients

In patients with moderate or severe renal impairment (creatinine clearance <50 mL/min) who are receiving an intravenous infusion of Voriconazole for injection, accumulation of the intravenous vehicle, hydroxypropyl β-cyclodextrin (HPβCD), occurs. Serum creatinine levels should be closely monitored in these patients, and, if increases occur, consideration should be given to changing to oral voriconazole therapy. [see Warnings and Precautions (5.7)].

Voriconazole and the intravenous vehicle, HPβCD, are dialyzable. A 4-hour hemodialysis session does not remove a sufficient amount of voriconazole to warrant dose adjustment [see Clinical Pharmacology (12.3)].

Pediatric Patients

Dosage adjustment of Voriconazole for injection in pediatric patients with renal impairment has not been established [see Use in Specific Populations (8.4)].

2.7 Dosage Adjustment When Co-Administered With Phenytoin or Efavirenz

The maintenance dose of voriconazole should be increased when co-administered with phenytoin or efavirenz. Use the optimal method for titrating dosage [see Drug Interactions (7) and Dosage and Administration (2.3)].

2.8 Preparation and Intravenous Administration of Voriconazole for Injection

Reconstitution

The powder is reconstituted with 19 mL of Water for Injection to obtain an extractable volume of 20 mL of clear concentrate containing 10 mg/mL of voriconazole. It is recommended that a standard 20 mL (non-automated) syringe be used to ensure that the exact amount (19.0 mL) of Water for Injection is dispensed. Discard the vial if a vacuum does not pull the diluent into the vial. Shake the vial until all the powder is dissolved.

Voriconazole for injection is an unpreserved sterile lyophile in a single dose vial. Therefore, from a microbiological point of view, once reconstituted, the product should be used immediately. If not used immediately, in-use storage times and conditions prior to use are the responsibility of the user and should not be longer than 24 hours at 2° to 8°C (36° to 46°F).

Dilution

Voriconazole for injection must be infused over 1 to 3 hours, at a concentration of 5 mg/mL or less. Therefore, the required volume of the 10 mg/mL Voriconazole for injection concentrate should be further diluted as follows (appropriate diluents listed below):

1. Calculate the volume of 10 mg/mL Voriconazole for injection concentrate required based on the patient's weight (see Table 2).
2. In order to allow the required volume of Voriconazole for injection concentrate to be added, withdraw and discard at least an equal volume of diluent from the infusion bag or bottle to be used. The volume of diluent remaining in the bag or bottle should be such that when the 10 mg/mL Voriconazole for injection concentrate is added, the final concentration is not less than 0.5 mg/mL nor greater than 5 mg/mL.
3. Using a suitable size syringe and aseptic technique, withdraw the required volume of Voriconazole for injection concentrate from the appropriate number of vials and add to the infusion bag or bottle. Discard Partially Used Vials.

The final Voriconazole for injection solution must be infused over 1 to 3 hours at a maximum rate of 3 mg/kg per hour.

Table 2: Required Volumes of 10 mg/mL Voriconazole for injection Concentrate
Body Weight (kg) | Volume of Voriconazole for injection Concentrate (10 mg/mL) required for:
Body Weight (kg) | 3 mg/kg dose (number of vials) | 4 mg/kg dose (number of vials) | 6 mg/kg dose (number of vials)
30 | 9 mL (1) | 12 mL (1) | 18 mL (1)
35 | 10.5 mL (1) | 14 mL (1) | 21 mL (2)
40 | 12 mL (1) | 16 mL (1) | 24 mL (2)
45 | 13.5 mL (1) | 18 mL (1) | 27 mL (2)
50 | 15 mL (1) | 20 mL (1) | 30 mL (2)
55 | 16.5 mL (1) | 22 mL (2) | 33 mL (2)
60 | 18 mL (1) | 24 mL (2) | 36 mL (2)
65 | 19.5 mL (1) | 26 mL (2) | 39 mL (2)
70 | 21 mL (2) | 28 mL (2) | 42 mL (3)
75 | 22.5 mL (2) | 30 mL (2) | 45 mL (3)
80 | 24 mL (2) | 32 mL (2) | 48 mL (3)
85 | 25.5 mL (2) | 34 mL (2) | 51 mL (3)
90 | 27 mL (2) | 36 mL (2) | 54 mL (3)
95 | 28.5 mL (2) | 38 mL (2) | 57 mL (3)
100 | 30 mL (2) | 40 mL (2) | 60 mL (3)

Voriconazole for injection is a single-dose unpreserved sterile lyophile. Therefore, from a microbiological point of view, once reconstituted, the product should be used immediately. If not used immediately, in-use storage times and conditions prior to use are the responsibility of the user and should not be longer than 24 hours at 2°C to 8°C (36°F to 46°F). This medicinal product is for single use only and any unused solution should be discarded. Only clear solutions without particles should be used.

The reconstituted solution can be diluted with:

0.9% Sodium Chloride USP
Lactated Ringers USP
5% Dextrose and Lactated Ringers USP
5% Dextrose and 0.45%
Sodium Chloride USP
5% Dextrose USP
5% Dextrose and 20 mEq Potassium Chloride USP
0.45% Sodium Chloride USP
5% Dextrose and 0.9% Sodium Chloride USP

The compatibility of Voriconazole for injection with diluents other than those described above is unknown (see Incompatibilities below).

Parenteral drug products should be inspected visually for particulate matter and discoloration prior to administration, whenever solution and container permit.

Incompatibilities

Voriconazole for injection must not be diluted with 4.2% Sodium Bicarbonate Infusion. The mildly alkaline nature of this diluent caused slight degradation of Voriconazole for injection after 24 hours storage at room temperature. Although refrigerated storage is recommended following reconstitution, use of this diluent is not recommended as a precautionary measure. Compatibility with other concentrations is unknown.

Additional pediatric use information is approved for PF PRISM C.V.'s VFEND (voriconazole) for injection. However, due to PF PRISM C.V.'s marketing exclusivity rights, this drug product is not labeled with that information.

3 DOSAGE FORMS AND STRENGTHS

Powder for Solution for Injection

Voriconazole for injection is supplied in a single-dose vial as a sterile lyophilized white to off white cake or powder equivalent to 200 mg voriconazole and 3,200 mg hydroxypropyl β-cyclodextrin (HPβCD).

4 CONTRAINDICATIONS

- Voriconazole for injection is contraindicated in patients with known hypersensitivity to voriconazole or its excipients. There is no information regarding cross-sensitivity between Voriconazole for injection (voriconazole) and other azole antifungal agents. Caution should be used when prescribing Voriconazole for injection to patients with hypersensitivity to other azoles.
- Coadministration of pimozide, quinidine or ivabradine with Voriconazole for injection is contraindicated because increased plasma concentrations of these drugs can lead to QT prolongation and rare occurrences of torsade de pointes [see Drug Interactions (7)].
- Coadministration of Voriconazole for injection with sirolimus is contraindicated because Voriconazole for injection significantly increases sirolimus concentrations [see Drug Interactions (7) and Clinical Pharmacology (12.3)].
- Coadministration of Voriconazole for injection with rifampin, carbamazepine, long-acting barbiturates and St. John's Wort is contraindicated because these drugs are likely to decrease plasma voriconazole concentrations significantly [see Drug Interactions (7) and Clinical Pharmacology (12.3)].
- Coadministration of standard doses of voriconazole with efavirenz doses of 400 mg every 24 hours or higher is contraindicated, because efavirenz significantly decreases plasma voriconazole concentrations in healthy subjects at these doses. Voriconazole also significantly increases efavirenz plasma concentrations [see Drug Interactions (7) and Clinical Pharmacology (12.3)].
- Coadministration of Voriconazole for injection with high-dose ritonavir (400 mg every 12 hours) is contraindicated because ritonavir (400 mg every 12 hours) significantly decreases plasma voriconazole concentrations. Coadministration of voriconazole and low-dose ritonavir (100 mg every 12 hours) should be avoided, unless an assessment of the benefit/risk to the patient justifies the use of voriconazole [see Drug Interactions (7) and Clinical Pharmacology (12.3)].
- Coadministration of Voriconazole for injection with rifabutin is contraindicated since Voriconazole for injection significantly increases rifabutin plasma concentrations and rifabutin also significantly decreases voriconazole plasma concentrations [see Drug Interactions (7) and Clinical Pharmacology (12.3)].
- Coadministration of Voriconazole for injection with ergot alkaloids (ergotamine and dihydroergotamine) is contraindicated because Voriconazole for injection may increase the plasma concentration of ergot alkaloids, which may lead to ergotism [see Drug Interactions (7)].
- Coadministration of Voriconazole for injection with naloxegol is contraindicated because Voriconazole for injection may increase plasma concentrations of naloxegol which may precipitate opioid withdrawal symptoms [see Drug Interactions (7)].
- Coadministration of Voriconazole for injection with tolvaptan is contraindicated because Voriconazole for injection may increase tolvaptan plasma concentrations and increase risk of adverse reactions [see Drug Interactions (7)].
- Coadministration of Voriconazole for injection with venetoclax at initiation and during the ramp-up phase is contraindicated in patients with chronic lymphocytic leukemia (CLL) or small lymphocytic lymphoma (SLL) due to the potential for increased risk of tumor lysis syndrome [see Drug Interactions (7)].
- Coadministration of Voriconazole for injection with lurasidone is contraindicated since it may result in significant increases in lurasidone exposure and the potential for serious adverse reactions [see Drug Interactions (7)].

5 WARNINGS AND PRECAUTIONS

5.1 Hepatic Toxicity

In clinical trials, there have been uncommon cases of serious hepatic reactions during treatment with Voriconazole for injection (including clinical hepatitis, cholestasis and fulminant hepatic failure, including fatalities). Instances of hepatic reactions were noted to occur primarily in patients with serious underlying medical conditions (predominantly hematological malignancy). Hepatic reactions, including hepatitis and jaundice, have occurred among patients with no other identifiable risk factors. Liver dysfunction has usually been reversible on discontinuation of therapy [see Adverse Reactions (6.1)].

A higher frequency of liver enzyme elevations was observed in the pediatric population [see Adverse Reactions (6.1)]. Hepatic function should be monitored in both adult and pediatric patients.

Measure serum transaminase levels and bilirubin at the initiation of Voriconazole for injection therapy and monitor at least weekly for the first month of treatment. Monitoring frequency can be reduced to monthly during continued use if no clinically significant changes are noted. If liver function tests become markedly elevated compared to baseline, Voriconazole for injection should be discontinued unless the medical judgment of the benefit/risk of the treatment for the patient justifies continued use [see Dosage and Administration (2.5), and Adverse Reactions (6.1)].

5.2 Arrhythmias and QT Prolongation

Some azoles, including Voriconazole for injection, have been associated with prolongation of the QT interval on the electrocardiogram. During clinical development and post-marketing surveillance, there have been rare cases of arrhythmias, (including ventricular arrhythmias such as torsade de pointes), cardiac arrests and sudden deaths in patients taking Voriconazole for injection. These cases usually involved seriously ill patients with multiple confounding risk factors, such as history of cardiotoxic chemotherapy, cardiomyopathy, hypokalemia and concomitant medications that may have been contributory.

Voriconazole for injection should be administered with caution to patients with potentially proarrhythmic conditions, such as:

- Congenital or acquired QT prolongation
- Cardiomyopathy, in particular when heart failure is present
- Sinus bradycardia
- Existing symptomatic arrhythmias
- Concomitant medicinal product that is known to prolong QT interval [see Contraindications (4), Drug Interactions (7), and Clinical Pharmacology (12.3)]

Rigorous attempts to correct potassium, magnesium and calcium should be made before starting and during voriconazole therapy [see Clinical Pharmacology (12.3)].

5.3 Infusion Related Reactions

During infusion of the intravenous formulation of Voriconazole for injection in healthy subjects, anaphylactoid-type reactions, including flushing, fever, sweating, tachycardia, chest tightness, dyspnea, faintness, nausea, pruritus and rash, have occurred uncommonly. Symptoms appeared immediately upon initiating the infusion. Consideration should be given to stopping the infusion should these reactions occur.

5.4 Visual Disturbances

The effect of Voriconazole for injection on visual function is not known if treatment continues beyond 28 days. There have been post-marketing reports of prolonged visual adverse reactions, including optic neuritis and papilledema. If treatment continues beyond 28 days, visual function including visual acuity, visual field, and color perception should be monitored [see Adverse Reactions (6.2)].

5.5 Severe Cutaneous Adverse Reactions

Severe cutaneous adverse reactions (SCARs), such as Stevens-Johnson syndrome (SJS), toxic epidermal necrolysis (TEN), and drug reaction with eosinophilia and systemic symptoms (DRESS), which can be life-threatening or fatal, have been reported during treatment with Voriconazole for injection. If a patient develops a severe cutaneous adverse reaction, Voriconazole for injection should be discontinued [see Adverse Reactions (6.1, 6.2)].

5.6 Photosensitivity

Voriconazole for injection has been associated with photosensitivity skin reaction. Patients, including pediatric patients, should avoid exposure to direct sunlight during Voriconazole for injection treatment and should use measures such as protective clothing and sunscreen with high sun protection factor (SPF). If phototoxic reactions occur, the patient should be referred to a dermatologist and Voriconazole for injection discontinuation should be considered. If Voriconazole for injection is continued despite the occurrence of phototoxicity-related lesions, dermatologic evaluation should be performed on a systematic and regular basis to allow early detection and management of premalignant lesions. Squamous cell carcinoma of the skin (including cutaneous SCC in situ, or Bowen's disease) and melanoma have been reported during long-term Voriconazole for injection therapy in patients with photosensitivity skin reactions. If a patient develops a skin lesion consistent with premalignant skin lesions, squamous cell carcinoma or melanoma, Voriconazole for injection should be discontinued. In addition, Voriconazole for injection has been associated with photosensitivity related skin reactions such as pseudoporphyria, cheilitis, and cutaneous lupus erythematosus, as well as increased risk of skin toxicity with concomitant use of methotrexate, a drug associated with ultraviolet (UV) reactivation. There is the potential for this risk to be observed with other drugs associated with UV reactivation. Patients should avoid strong, direct sunlight during Voriconazole for injection therapy.

The frequency of phototoxicity reactions is higher in the pediatric population. Because squamous cell carcinoma has been reported in patients who experience photosensitivity reactions, stringent measures for photoprotection are warranted in children. In children experiencing photoaging injuries such as lentigines or ephelides, sun avoidance and dermatologic follow-up are recommended even after treatment discontinuation.

5.7 Renal Toxicity

Hydroxypropyl-β-cyclodextrin (HPβCD), the intravenous vehicle of Voriconazole for injection, is eliminated through glomerular filtration. Therefore, in patients with moderate to severe renal dysfunction (creatinine clearance <50 mL/min), accumulation of HPβCD occurs. Serum creatinine (Scr) levels should be closely monitored in patients with renal impairment. If increases in Scr occur, consideration should be given to changing to alternate antifungal therapy with similar coverage, unless an assessment of the benefit/risk to the patient justifies the continued use of intravenous Voriconazole for injection [see Dosage and Administration (2.6) and Clinical Pharmacology (12.3)].

Acute renal failure has been observed in patients undergoing treatment with Voriconazole for injection. Patients being treated with voriconazole are likely to be treated concomitantly with nephrotoxic medications and may have concurrent conditions that may result in decreased renal function.

Patients should be monitored for the development of abnormal renal function. This should include laboratory evaluation of serum creatinine [see Clinical Pharmacology (12.3) and Dosage and Administration (2.6)].

5.8 Adrenal Dysfunction

Reversible cases of azole-induced adrenal insufficiency have been reported in patients receiving azoles, including Voriconazole for injection. Adrenal insufficiency has been reported in patients receiving azoles with or without concomitant corticosteroids. In patients receiving azoles without corticosteroids adrenal insufficiency is related to direct inhibition of steroidogenesis by azoles. In patients taking corticosteroids, voriconazole associated CYP3A4 inhibition of their metabolism may lead to corticosteroid excess and adrenal suppression [see Drug Interactions (7) and Clinical Pharmacology (12.3)]. Cushing's syndrome with and without subsequent adrenal insufficiency has also been reported in patients receiving Voriconazole for injection concomitantly with corticosteroids.

Patients receiving Voriconazole for injection and corticosteroids (via all routes of administration) should be carefully monitored for adrenal dysfunction both during and after Voriconazole for injection treatment. Patients should be instructed to seek immediate medical care if they develop signs and symptoms of Cushing's syndrome or adrenal insufficiency.

5.9 Embryo-Fetal Toxicity

Voriconazole can cause fetal harm when administered to a pregnant woman.

In animals, voriconazole administration was associated with fetal malformations, embryotoxicity, increased gestational length, dystocia and embryomortality [see Use in Specific Populations (8.1)].

If Voriconazole for injection is used during pregnancy, or if the patient becomes pregnant while taking Voriconazole for injection, inform the patient of the potential hazard to the fetus. Advise females of reproductive potential to use effective contraception during treatment with Voriconazole for injection [see Use in Specific Populations (8.3)].

5.10 Laboratory Tests

Electrolyte disturbances such as hypokalemia, hypomagnesemia and hypocalcemia should be corrected prior to initiation of and during Voriconazole for injection therapy.

Patient management should include laboratory evaluation of renal (particularly serum creatinine) and hepatic function (particularly liver function tests and bilirubin).

5.11 Pancreatitis

Pancreatitis has been observed in patients undergoing treatment with Voriconazole for injection [see Adverse Reactions (6.1, 6.2)].

Patients with risk factors for acute pancreatitis (e.g., recent chemotherapy, hematopoietic stem cell transplantation [HSCT]) should be monitored for the development of pancreatitis during Voriconazole for injection treatment.

5.12 Skeletal Adverse Reactions

Fluorosis and periostitis have been reported during long-term Voriconazole for injection therapy. If a patient develops skeletal pain and radiologic findings compatible with fluorosis or periostitis, Voriconazole for injection should be discontinued [see Adverse Reactions (6.2)].

5.13 Clinically Significant Drug Interactions

See Table 6 for a listing of drugs that may significantly alter voriconazole concentrations. Also, see Table 7 for a listing of drugs that may interact with voriconazole resulting in altered pharmacokinetics or pharmacodynamics of the other drug [see Contraindications (4) and Drug Interactions (7)].

6 ADVERSE REACTIONS

The following serious adverse reactions are described elsewhere in the labeling:

Hepatic Toxicity [see Warnings and Precautions (5.1)]

Arrhythmias and QT Prolongation [see Warnings and Precautions (5.2)]

Infusion Related Reactions [see Warnings and Precautions (5.3)]

Visual Disturbances [see Warnings and Precautions (5.4)]

Severe Cutaneous Adverse Reactions [see Warnings and Precautions (5.5)]

Photosensitivity [see Warnings and Precautions (5.6)]

Renal Toxicity [see Warnings and Precautions (5.7)]

6.1 Clinical Trials Experience

Because clinical trials are conducted under widely varying conditions, adverse reaction rates observed in clinical trials of a drug cannot be directly compared to rates in the clinical trials of another drug and may not reflect the rates observed in practice.

Clinical Trials Experience in Adults

Overview

The most frequently reported adverse reactions (see Table 3) in the adult therapeutic trials were visual disturbances (18.7%), fever (5.7%), nausea (5.4%), rash (5.3%), vomiting (4.4%), chills (3.7%), headache (3.0%), liver function test increased (2.7%), tachycardia (2.4%), hallucinations (2.4%). The adverse reactions which most often led to discontinuation of voriconazole therapy were elevated liver function tests, rash, and visual disturbances [see Warning and Precautions (5.1, 5.4), and Adverse Reactions (6.1)].

The data described in Table 3 reflect exposure to voriconazole in 1655 patients in the nine therapeutic studies. This represents a heterogeneous population, including immunocompromised patients, e.g., patients with hematological malignancy or HIV and non-neutropenic patients. This subgroup does not include healthy subjects and patients treated in the compassionate use and non-therapeutic studies. This patient population was 62% male, had a mean age of 46 years (range 11–90, including 51 patients aged 12–18 years), and was 78% White and 10% Black. Five hundred sixty one patients had a duration of voriconazole therapy of greater than 12 weeks, with 136 patients receiving voriconazole for over six months. Table 3 includes all adverse reactions which were reported at an incidence of ≥2% during voriconazole therapy in the all therapeutic studies population, studies 307/602 and 608 combined, as well as events of concern which occurred at an incidence of <2%.

In study 307/602, 381 patients (196 on voriconazole, 185 on amphotericin B) were treated to compare voriconazole to amphotericin B followed by other licensed antifungal therapy (OLAT) in the primary treatment of patients with acute IA. The rate of discontinuation from voriconazole study medication due to adverse reactions was 21.4% (42/196 patients). In study 608, 403 patients with candidemia were treated to compare voriconazole (272 patients) to the regimen of amphotericin B followed by fluconazole (131 patients). The rate of discontinuation from voriconazole study medication due to adverse reactions was 19.5% out of 272 patients. Laboratory test abnormalities for these studies are discussed under Clinical Laboratory Values below.

Table 3: Adverse Reactions Rate ≥ 2% on Voriconazole or Adverse Reactions of Concern in Therapeutic Studies Population, Studies 307/602-608 Combined, Possibly Related to Therapy or Causality Unknown [Study 307/602: IA; Study 608: candidemia]
 | Therapeutic Studies [Studies 303, 304, 307, 309, 602, 603, 604, 608] | Studies 307/602 and 608
 | Voriconazole N=1655 | Voriconazole N=468 | Ampho B [Amphotericin B followed by other licensed antifungal therapy] N=185 | Ampho B→ Fluconazole N=131
 | N (%) | N (%) | N (%) | N (%)
Special Senses [See Warnings and Precautions (5.4)]
Abnormal vision | 310 (18.7) | 63 (13.5) | 1 (0.5) | 0
Photophobia | 37 (2.2) | 8 (1.7) | 0 | 0
Chromatopsia | 20 (1.2) | 2 (0.4) | 0 | 0
Body as a Whole
Fever | 94 (5.7) | 8 (1.7) | 25 (13.5) | 5 (3.8)
Chills | 61 (3.7) | 1 (0.2) | 36 (19.5) | 8 (6.1)
Headache | 49 (3.0) | 9 (1.9) | 8 (4.3) | 1 (0.8)
Cardiovascular System
Tachycardia | 39 (2.4) | 6 (1.3) | 5 (2.7) | 0
Digestive System
Nausea | 89 (5.4) | 18 (3.8) | 29 (15.7) | 2 (1.5)
Vomiting | 72 (4.4) | 15 (3.2) | 18 (9.7) | 1 (0.8)
Liver function tests abnormal | 45 (2.7) | 15 (3.2) | 4 (2.2) | 1 (0.8)
Cholestatic jaundice | 17 (1.0) | 8 (1.7) | 0 | 1 (0.8)
Metabolic and Nutritional Systems
Alkaline phosphatase increased | 59 (3.6) | 19 (4.1) | 4 (2.2) | 3 (2.3)
Hepatic enzymes increased | 30 (1.8) | 11 (2.4) | 5 (2.7) | 1 (0.8)
SGOT increased | 31 (1.9) | 9 (1.9) | 0 | 1 (0.8)
SGPT increased | 29 (1.8) | 9 (1.9) | 1 (0.5) | 2 (1.5)
Hypokalemia | 26 (1.6) | 3 (0.6) | 36 (19.5) | 16 (12.2)
Bilirubinemia | 15 (0.9) | 5 (1.1) | 3 (1.6) | 2 (1.5)
Creatinine increased | 4 (0.2) | 0 | 59 (31.9) | 10 (7.6)
Nervous System
Hallucinations | 39 (2.4) | 13 (2.8) | 1 (0.5) | 0
Skin and Appendages
Rash | 88 (5.3) | 20 (4.3) | 7 (3.8) | 1 (0.8)
Urogenital
Kidney function abnormal | 10 (0.6) | 6 (1.3) | 40 (21.6) | 9 (6.9)
Acute kidney failure | 7 (0.4) | 2 (0.4) | 11 (5.9) | 7 (5.3)

Visual Disturbances

Voriconazole for injection treatment-related visual disturbances are common. In therapeutic trials, approximately 21% of patients experienced abnormal vision, color vision change and/or photophobia. Visual disturbances may be associated with higher plasma concentrations and/or doses.

The mechanism of action of the visual disturbance is unknown, although the site of action is most likely to be within the retina. In a study in healthy subjects investigating the effect of 28-day treatment with voriconazole on retinal function, Voriconazole for injection caused a decrease in the electroretinogram (ERG) waveform amplitude, a decrease in the visual field, and an alteration in color perception. The ERG measures electrical currents in the retina. These effects were noted early in administration of Voriconazole for injection and continued through the course of study drug treatment. Fourteen days after end of dosing, ERG, visual fields and color perception returned to normal [see Warnings and Precautions (5.4)].

Dermatological Reactions

Dermatological reactions were common in the patients treated with Voriconazole for injection. The mechanism underlying these dermatologic adverse reactions remains unknown.

Severe cutaneous adverse reactions (SCARs), including Stevens-Johnson syndrome (SJS), toxic epidermal necrolysis (TEN), and drug reaction with eosinophilia and systemic symptoms (DRESS) have been reported during treatment with Voriconazole for injection. Erythema multiforme has also been reported during treatment with Voriconazole for injection [see Warnings and Precautions (5.5) and Adverse Reactions (6.2)].

Voriconazole has also been associated with additional photosensitivity related skin reactions such as pseudoporphyria, cheilitis, and cutaneous lupus erythematosus [see Warnings and Precautions (5.6) and Adverse Reactions (6.2)].

Less Common Adverse Reactions

The following adverse reactions occurred in <2% of all voriconazole-treated patients in all therapeutic studies (N=1655). This listing includes events where a causal relationship to voriconazole cannot be ruled out or those which may help the physician in managing the risks to the patients. The list does not include events included in Table 3 above and does not include every event reported in the voriconazole clinical program.

Body as a Whole: abdominal pain, abdomen enlarged, allergic reaction, anaphylactoid reaction [see Warnings and Precautions (5.3)], ascites, asthenia, back pain, chest pain, cellulitis, edema, face edema, flank pain, flu syndrome, graft versus host reaction, granuloma, infection, bacterial infection, fungal infection, injection site pain, injection site infection/inflammation, mucous membrane disorder, multi-organ failure, pain, pelvic pain, peritonitis, sepsis, substernal chest pain.

Cardiovascular: atrial arrhythmia, atrial fibrillation, AV block complete, bigeminy, bradycardia, bundle branch block, cardiomegaly, cardiomyopathy, cerebral hemorrhage, cerebral ischemia, cerebrovascular accident, congestive heart failure, deep thrombophlebitis, endocarditis, extrasystoles, heart arrest, hypertension, hypotension, myocardial infarction, nodal arrhythmia, palpitation, phlebitis, postural hypotension, pulmonary embolus, QT interval prolonged, supraventricular extrasystoles, supraventricular tachycardia, syncope, thrombophlebitis, vasodilatation, ventricular arrhythmia, ventricular fibrillation, ventricular tachycardia (including torsade de pointes) [see Warnings and Precautions (5.2)].

Digestive: anorexia, cheilitis, cholecystitis, cholelithiasis, constipation, diarrhea, duodenal ulcer perforation, duodenitis, dyspepsia, dysphagia, dry mouth, esophageal ulcer, esophagitis, flatulence, gastroenteritis, gastrointestinal hemorrhage, GGT/LDH elevated, gingivitis, glossitis, gum hemorrhage, gum hyperplasia, hematemesis, hepatic coma, hepatic failure, hepatitis, intestinal perforation, intestinal ulcer, jaundice, enlarged liver, melena, mouth ulceration, pancreatitis, parotid gland enlargement, periodontitis, proctitis, pseudomembranous colitis, rectal disorder, rectal hemorrhage, stomach ulcer, stomatitis, tongue edema.

Endocrine: adrenal cortex insufficiency, diabetes insipidus, hyperthyroidism, hypothyroidism.

Hemic and Lymphatic: agranulocytosis, anemia (macrocytic, megaloblastic, microcytic, normocytic), aplastic anemia, hemolytic anemia, bleeding time increased, cyanosis, DIC, ecchymosis, eosinophilia, hypervolemia, leukopenia, lymphadenopathy, lymphangitis, marrow depression, pancytopenia, petechia, purpura, enlarged spleen, thrombocytopenia, thrombotic thrombocytopenic purpura.

Metabolic and Nutritional: albuminuria, BUN increased, creatine phosphokinase increased, edema, glucose tolerance decreased, hypercalcemia, hypercholesteremia, hyperglycemia, hyperkalemia, hypermagnesemia, hypernatremia, hyperuricemia, hypocalcemia, hypoglycemia, hypomagnesemia, hyponatremia, hypophosphatemia, peripheral edema, uremia.

Musculoskeletal: arthralgia, arthritis, bone necrosis, bone pain, leg cramps, myalgia, myasthenia, myopathy, osteomalacia, osteoporosis.

Nervous System: abnormal dreams, acute brain syndrome, agitation, akathisia, amnesia, anxiety, ataxia, brain edema, coma, confusion, convulsion, delirium, dementia, depersonalization, depression, diplopia, dizziness, encephalitis, encephalopathy, euphoria, Extrapyramidal Syndrome, grand mal convulsion, Guillain-Barré syndrome, hypertonia, hypesthesia, insomnia, intracranial hypertension, libido decreased, neuralgia, neuropathy, nystagmus, oculogyric crisis, paresthesia, psychosis, somnolence, suicidal ideation, tremor, vertigo.

Respiratory System: cough increased, dyspnea, epistaxis, hemoptysis, hypoxia, lung edema, pharyngitis, pleural effusion, pneumonia, respiratory disorder, respiratory distress syndrome, respiratory tract infection, rhinitis, sinusitis, voice alteration.

Skin and Appendages: alopecia, angioedema, contact dermatitis, discoid lupus erythematosis, eczema, erythema multiforme, exfoliative dermatitis, fixed drug eruption, furunculosis, herpes simplex, maculopapular rash, melanoma, melanosis, photosensitivity skin reaction, pruritus, pseudoporphyria, psoriasis, skin discoloration, skin disorder, skin dry, Stevens-Johnson syndrome, squamous cell carcinoma (including cutaneous SCC in situ, or Bowen's disease), sweating, toxic epidermal necrolysis, urticaria.

Special Senses: abnormality of accommodation, blepharitis, color blindness, conjunctivitis, corneal opacity, deafness, ear pain, eye pain, eye hemorrhage, dry eyes, hypoacusis, keratitis, keratoconjunctivitis, mydriasis, night blindness, optic atrophy, optic neuritis, otitis externa, papilledema, retinal hemorrhage, retinitis, scleritis, taste loss, taste perversion, tinnitus, uveitis, visual field defect.

Urogenital: anuria, blighted ovum, creatinine clearance decreased, dysmenorrhea, dysuria, epididymitis, glycosuria, hemorrhagic cystitis, hematuria, hydronephrosis, impotence, kidney pain, kidney tubular necrosis, metrorrhagia, nephritis, nephrosis, oliguria, scrotal edema, urinary incontinence, urinary retention, urinary tract infection, uterine hemorrhage, vaginal hemorrhage.

Clinical Laboratory Values in Adults

The overall incidence of transaminase increases >3× upper limit of normal (not necessarily comprising an adverse reaction) was 17.7% (268/1514) in adult subjects treated with Voriconazole for injection for therapeutic use in pooled clinical trials. Increased incidence of liver function test abnormalities may be associated with higher plasma concentrations and/or doses. The majority of abnormal liver function tests either resolved during treatment without dose adjustment or resolved following dose adjustment, including discontinuation of therapy.

Voriconazole for injection has been infrequently associated with cases of serious hepatic toxicity including cases of jaundice and rare cases of hepatitis and hepatic failure leading to death. Most of these patients had other serious underlying conditions.

Liver function tests should be evaluated at the start of and during the course of Voriconazole for injection therapy. Patients who develop abnormal liver function tests during Voriconazole for injection therapy should be monitored for the development of more severe hepatic injury. Patient management should include laboratory evaluation of hepatic function (particularly liver function tests and bilirubin). Discontinuation of Voriconazole for injection must be considered if clinical signs and symptoms consistent with liver disease develop that may be attributable to Voriconazole for injection [see Warnings and Precautions (5.1)].

Acute renal failure has been observed in severely ill patients undergoing treatment with Voriconazole for injection. Patients being treated with Voriconazole for injection are likely to be treated concomitantly with nephrotoxic medications and have concurrent conditions that can result in decreased renal function. It is recommended that patients are monitored for the development of abnormal renal function. This should include laboratory evaluation of serum creatinine.

Tables 4 to 5 show the number of patients with hypokalemia and clinically significant changes in renal and liver function tests in two randomized, comparative multicenter studies. In study 307/602, patients with definite or probable IA were randomized to either voriconazole or amphotericin B therapy. In study 608, patients with candidemia were randomized to either voriconazole or the regimen of amphotericin B followed by fluconazole.

Table 4: Study 307/602 – Primary Treatment of Invasive Aspergillosis Clinically Significant Laboratory Test Abnormalities
 | Criteria [Without regard to baseline value] | Voriconazole | Amphotericin B [Amphotericin B followed by other licensed antifungal therapy]
 |  | n/N (%) | n/N (%)
T. Bilirubin | >1.5× ULN | 35/180 (19.4) | 46/173 (26.6)
AST | >3.0× ULN | 21/180 (11.7) | 18/174 (10.3)
ALT | >3.0× ULN | 34/180 (18.9) | 40/173 (23.1)
Alkaline Phosphatase | >3.0× ULN | 29/181 (16.0) | 38/173 (22.0)
Creatinine | >1.3× ULN | 39/182 (21.4) | 102/177 (57.6)
Potassium | <0.9× LLN | 30/181 (16.6) | 70/178 (39.3)
n = number of patients with a clinically significant abnormality while on study therapy
N = total number of patients with at least one observation of the given lab test while on study therapy
AST = Aspartate aminotransferase; ALT = alanine aminotransferase
ULN = upper limit of normal
LLN = lower limit of normal

Table 5: Protocol 608 – Treatment of Candidemia Clinically Significant Laboratory Test Abnormalities
 | Criteria [Without regard to baseline value] | Voriconazole | Amphotericin B followed by Fluconazole
 |  | n/N (%) | n/N (%)
T. Bilirubin | >1.5× ULN | 50/261 (19.2) | 31/115 (27.0)
AST | >3.0× ULN | 40/261 (15.3) | 16/116 (13.8)
ALT | >3.0× ULN | 22/261 (8.4) | 15/116 (12.9)
Alkaline Phosphatase | >3.0× ULN | 59/261 (22.6) | 26/115 (22.6)
Creatinine | >1.3× ULN | 39/260 (15.0) | 32/118 (27.1)
Potassium | <0.9× LLN | 43/258 (16.7) | 35/118 (29.7)
n = number of patients with a clinically significant abnormality while on study therapy
N = total number of patients with at least one observation of the given lab test while on study therapy
AST = Aspartate aminotransferase; ALT = alanine aminotransferase
ULN = upper limit of normal
LLN = lower limit of normal

Clinical Trials Experience in Pediatric Patients

The safety of Voriconazole for injection was investigated in pediatric patients, including 51 pediatric patients aged 12 to less than 18 years of age who were enrolled in the adult therapeutic studies.

Hepatic-Related Adverse Reactions in Pediatric Patients

The frequency of hepatic-related adverse reactions in pediatric patients exposed to Voriconazole for injection in therapeutic studies was numerically higher than that of adults (28.6% compared to 24.1%, respectively). The higher frequency of hepatic adverse reactions in the pediatric population was mainly due to an increased frequency of liver enzyme elevations (21.9% in pediatric patients compared to 16.1% in adults), including transaminase elevations (ALT and AST combined) 7.6% in the pediatric patients compared to 5.1% in adults.

Additional pediatric use information is approved for PF PRISM C.V.'s VFEND (voriconazole) for injection. However, due to PF PRISM C.V.'s marketing exclusivity rights, this drug product is not labeled with that information.

6.2 Postmarketing Experience in Adult and Pediatric Patients

The following adverse reactions have been identified during post-approval use of Voriconazole for injection. Because these reactions are reported voluntarily from a population of uncertain size, it is not always possible to reliably estimate their frequency or establish a causal relationship to drug exposure.

Dermatological Reactions

Increased risk of skin toxicity with concomitant use of methotrexate, a drug associated with UV reactivation, was observed in postmarketing reports [see Warnings and Precautions (5.6) and Adverse Reactions (6.1)].

Adults

Skeletal: fluorosis and periostitis have been reported during long-term voriconazole therapy [see Warnings and Precautions (5.11)].

Eye disorders: prolonged visual adverse reactions, including optic neuritis and papilledema [see Warnings and Precautions (5.4)].

Skin and Appendages: drug reaction with eosinophilia and systemic symptoms (DRESS) has been reported [see Warnings and Precautions (5.5) and Adverse Reactions (6.1)].

Endocrine disorders: adrenal insufficiency, Cushing's syndrome (when voriconazole has been used concomitantly with corticosteroids) [see Warnings and Precautions (5.8)].

Pediatric Patients

There have been postmarketing reports of pancreatitis in pediatric patients.

7 DRUG INTERACTIONS

Voriconazole is metabolized by cytochrome P450 isoenzymes, CYP2C19, CYP2C9, and CYP3A4. Therefore, inhibitors or inducers of these isoenzymes may increase or decrease voriconazole plasma concentrations, respectively. Voriconazole is a strong inhibitor of CYP3A4, and also inhibits CYP2C19 and CYP2C9. Therefore, voriconazole may increase the plasma concentrations of substances metabolized by these CYP450 isoenzymes.

Tables 6 and 7 provide the clinically significant interactions between voriconazole and other medical products.

Table 6: Effect of Other Drugs on Voriconazole Pharmacokinetics [see Clinical Pharmacology (12.3)]
Drug/Drug Class (Mechanism of Interaction by the Drug) | Voriconazole Plasma Exposure (Cmax and AUCτ after 200 mg every 12 hours) | Recommendations for Voriconazole Dosage Adjustment/Comments
Rifampin and Rifabutin (CYP450 Induction) | Significantly Reduced | Contraindicated
Efavirenz (400 mg every 24 hours) (CYP450 Induction) | Significantly Reduced | Contraindicated
High-dose Ritonavir (400 mg every 12 hours) (CYP450 Induction) | Significantly Reduced | Contraindicated
Low-dose Ritonavir (100 mg every 12 hours) (CYP450 Induction) | Reduced | Coadministration of voriconazole and low-dose ritonavir (100 mg every 12 hours) should be avoided, unless an assessment of the benefit/risk to the patient justifies the use of voriconazole
Carbamazepine (CYP450 Induction) | Not Studied In Vivo or In Vitro, but Likely to Result in Significant Reduction | Contraindicated
Long Acting Barbiturates (e.g., phenobarbital, mephobarbital) (CYP450 Induction) | Not Studied In Vivo or In Vitro, but Likely to Result in Significant Reduction | Contraindicated
Phenytoin (CYP450 Induction) | Significantly Reduced | Increase voriconazole maintenance dose from 4 mg/kg to 5 mg/kg IV every12 hours
Letermovir (CYP2C9/2C19 Induction) | Reduced | If concomitant administration of voriconazole with letermovir cannot be avoided, monitor for reduced effectiveness of voriconazole.
St. John's Wort (CYP450 inducer; P-gp inducer) | Significantly Reduced | Contraindicated
Oral Contraceptives containing ethinyl estradiol and norethindrone (CYP2C19 Inhibition) | Increased | Monitoring for adverse reactions and toxicity related to voriconazole is recommended when coadministered with oral contraceptives
Fluconazole (CYP2C9, CYP2C19 and CYP3A4 Inhibition) | Significantly Increased | Avoid concomitant administration of voriconazole and fluconazole. Monitoring for adverse reactions and toxicity related to voriconazole is started within 24 hours after the last dose of fluconazole
Other HIV Protease Inhibitors (CYP3A4 Inhibition) | In Vivo Studies Showed No Significant Effects of Indinavir on Voriconazole Exposure | No dosage adjustment in the voriconazole dosage needed when coadministered with indinavir.
Other HIV Protease Inhibitors (CYP3A4 Inhibition) | In Vitro Studies Demonstrated Potential for Inhibition of Voriconazole Metabolism (Increased Plasma Exposure) | Frequent monitoring for adverse reactions and toxicity related to voriconazole when coadministered with other HIV protease inhibitors
Other NNRTIs [Non-Nucleoside Reverse Transcriptase Inhibitors] (CYP3A4 Inhibition or CYP450 Induction) | In Vitro Studies Demonstrated Potential for Inhibition of Voriconazole Metabolism by Delavirdine and Other NNRTIs (Increased Plasma Exposure). | Frequent monitoring for adverse reactions and toxicity related to voriconazole
Other NNRTIs [Non-Nucleoside Reverse Transcriptase Inhibitors] (CYP3A4 Inhibition or CYP450 Induction) | A Voriconazole-Efavirenz Drug Interaction Study Demonstrated the Potential for the Metabolism of Voriconazole to be Induced by Efavirenz and Other NNRTIs (Decreased Plasma Exposure) | Careful assessment of voriconazole effectiveness

Table 7: Effect of Voriconazole on Pharmacokinetics of Other Drugs [see Clinical Pharmacology (12.3)]
Drug/Drug Class (Mechanism of Interaction by Voriconazole) | Drug Plasma Exposure (Cmax and AUCτ) | Recommendations for Drug Dosage Adjustment/Comments
Sirolimus (CYP3A4 Inhibition) | Significantly Increased | Contraindicated
Rifabutin (CYP3A4 Inhibition) | Significantly Increased | Contraindicated
Efavirenz (400 mg every 24 hours) (CYP3A4 Inhibition) | Significantly Increased | Contraindicated
High-dose Ritonavir (400 mg every 12 hours) (CYP3A4 Inhibition) | No Significant Effect of Voriconazole on Ritonavir Cmax or AUCτ | Contraindicated because of significant reduction of voriconazole Cmax and AUCτ
Low-dose Ritonavir (100 mg every 12 hours) | Slight Decrease in Ritonavir Cmax and AUCτ | Coadministration of voriconazole and low-dose ritonavir (100 mg every 12 hours) should be avoided (due to the reduction in voriconazole Cmax and AUCτ) unless an assessment of the benefit/risk to the patient justifies the use of voriconazole
Pimozide, Quinidine, Ivabradine (CYP3A4 Inhibition) | Not Studied In Vivo or In Vitro, but Drug Plasma Exposure Likely to be Increased | Contraindicated because of potential for QT prolongation and rare occurrence of torsade de pointes
Ergot Alkaloids (CYP450 Inhibition) | Not Studied In Vivo or In Vitro, but Drug Plasma Exposure Likely to be Increased | Contraindicated
Naloxegol (CYP3A4 Inhibition) | Not Studied In Vivo or In Vitro, but Drug Plasma Exposure Likely to be Increased which may Increase the Risk of Adverse Reactions | Contraindicated
Tolvaptan (CYP3A4 Inhibition) | Although Not Studied Clinically, Voriconazole is Likely to Significantly Increase the Plasma Concentrations of Tolvaptan | Contraindicated
Venetoclax (CYP3A4 Inhibition) | Not studied In Vivo or In Vitro, but Venetoclax Plasma Exposure Likely to be Significantly Increased | Coadministration of voriconazole is contraindicated at initiation and during the ramp-up phase in patients with chronic lymphocytic leukemia (CLL) or small lymphocytic lymphoma (SLL). Refer to the venetoclax labeling for safety monitoring and dose reduction in the steady daily dosing phase in CLL/SLL patients. For patients with acute myeloid leukemia (AML), dose reduction and safety monitoring are recommended across all dosing phases when coadministering Voriconazole for injection with venetoclax. Refer to the venetoclax prescribing information for dosing instructions.
Lemborexant (CYP3A4 Inhibition) | Not Studied In Vivo or In Vitro, but Drug Plasma Exposure Likely to be Increased | Avoid concomitant use of Voriconazole for injection with lemborexant.
Glasdegib (CYP3A4 Inhibition) | Not Studied In Vivo or In Vitro, but Drug Plasma Exposure Likely to be Increased | Consider alternative therapies. If concomitant use cannot be avoided, monitor patients for increased risk of adverse reactions including QTc interval prolongation.
Tyrosine kinase inhibitors (including but not limited to axitinib, bosutinib, cabozantinib, ceritinib, cobimetinib, dabrafenib, dasatinib, nilotinib, sunitinib, ibrutinib, ribociclib) (CYP3A4 Inhibition) | Not Studied In Vivo or In Vitro, but Drug Plasma Exposure Likely to be Increased | Avoid concomitant use of Voriconazole for injection. If concomitant use cannot be avoided, dose reduction of the tyrosine kinase inhibitor is recommended. Refer to the prescribing information for the relevant product.
Lurasidone (CYP3A4 Inhibition) | Not Studied In Vivo or In Vitro, but Voriconazole is Likely to Significantly Increase the Plasma Concentrations of Lurasidone | Contraindicated
Cyclosporine (CYP3A4 Inhibition) | AUCτ Significantly Increased; No Significant Effect on Cmax | When initiating therapy with Voriconazole for injection in patients already receiving cyclosporine, reduce the cyclosporine dose to one-half of the starting dose and follow with frequent monitoring of cyclosporine blood levels. Increased cyclosporine levels have been associated with nephrotoxicity. When Voriconazole for injection is discontinued, cyclosporine concentrations must be frequently monitored and the dose increased as necessary.
Methadone (CYP3A4 Inhibition) | Increased | Increased plasma concentrations of methadone have been associated with toxicity including QT prolongation. Frequent monitoring for adverse reactions and toxicity related to methadone is recommended during coadministration. Dose reduction of methadone may be needed.
Fentanyl (CYP3A4 Inhibition) | Increased | Reduction in the dose of fentanyl and other long-acting opiates metabolized by CYP3A4 should be considered when coadministered with Voriconazole for injection. Extended and frequent monitoring for opiate-associated adverse reactions may be necessary.
Alfentanil (CYP3A4 Inhibition) | Significantly Increased | An increase in the incidence of delayed and persistent alfentanil-associated nausea and vomiting were observed when coadministered with Voriconazole for injection. Reduction in the dose of alfentanil and other opiates metabolized by CYP3A4 (e.g., sufentanil) should be considered when coadministered with Voriconazole for injection. A longer period for monitoring respiratory and other opiate-associated adverse reactions may be necessary.
Oxycodone (CYP3A4 Inhibition) | Significantly Increased | Increased visual effects (heterophoria and miosis) of oxycodone were observed when coadministered with Voriconazole for injection. Reduction in the dose of oxycodone and other long-acting opiates metabolized by CYP3A4 should be considered when coadministered with Voriconazole for injection. Extended and frequent monitoring for opiate-associated adverse reactions may be necessary.
NSAIDs [Non-Steroidal Anti-Inflammatory Drug] including ibuprofen and diclofenac (CYP2C9 Inhibition) | Increased | Frequent monitoring for adverse reactions and toxicity related to NSAIDs. Dose reduction of NSAIDs may be needed.
Tacrolimus (CYP3A4 Inhibition) | Significantly Increased | When initiating therapy with Voriconazole for injection in patients already receiving tacrolimus, reduce the tacrolimus dose to one-third of the starting dose and follow with frequent monitoring of tacrolimus blood levels. Increased tacrolimus levels have been associated with nephrotoxicity. When Voriconazole for injection is discontinued, tacrolimus concentrations must be frequently monitored and the dose increased as necessary.
Phenytoin (CYP2C9 Inhibition) | Significantly Increased | Frequent monitoring of phenytoin plasma concentrations and frequent monitoring of adverse effects related to phenytoin.
Oral Contraceptives containing ethinyl estradiol and norethindrone (CYP3A4 Inhibition) | Increased | Monitoring for adverse reactions related to oral contraceptives is recommended during coadministration.
Prednisolone and other corticosteroids (CYP3A4 Inhibition) | In Vivo Studies Showed No Significant Effects of Voriconazole for injection on Prednisolone Exposure | No dosage adjustment for prednisolone when coadministered with Voriconazole for injection [see Clinical Pharmacology (12.3)].
Prednisolone and other corticosteroids (CYP3A4 Inhibition) | Not Studied In vitro or In vivo for Other Corticosteroids, but Drug Exposure Likely to be Increased | Monitor for potential adrenal dysfunction when Voriconazole for injection is administered with other corticosteroids [see Warnings and Precautions (5.8)].
Warfarin (CYP2C9 Inhibition) | Prothrombin Time Significantly Increased | If patients receiving coumarin preparations are treated simultaneously with voriconazole, the prothrombin time or other suitable anticoagulation tests should be monitored at close intervals and the dosage of anticoagulants adjusted accordingly.
Other Oral Coumarin Anticoagulants (CYP2C9/3A4 Inhibition) | Not Studied In Vivo or In Vitro for other Oral Coumarin Anticoagulants, but Drug Plasma Exposure Likely to be Increased | If patients receiving coumarin preparations are treated simultaneously with voriconazole, the prothrombin time or other suitable anticoagulation tests should be monitored at close intervals and the dosage of anticoagulants adjusted accordingly.
Ivacaftor (CYP3A4 Inhibition) | Not Studied In Vivo or In Vitro, but Drug Plasma Exposure Likely to be Increased which may Increase the Risk of Adverse Reactions | Dose reduction of ivacaftor is recommended. Refer to the prescribing information for ivacaftor
Eszopiclone (CYP3A4 Inhibition) | Not Studied In Vivo or In Vitro, but Drug Plasma Exposure Likely to be Increased which may Increase the Sedative Effect of Eszopiclone | Dose reduction of eszopiclone is recommended. Refer to the prescribing information for eszopiclone.
Omeprazole (CYP2C19/3A4 Inhibition) | Significantly Increased | When initiating therapy with Voriconazole for injection in patients already receiving omeprazole doses of 40 mg or greater, reduce the omeprazole dose by one-half. The metabolism of other proton pump inhibitors that are CYP2C19 substrates may also be inhibited by voriconazole and may result in increased plasma concentrations of other proton pump inhibitors.
Other HIV Protease Inhibitors (CYP3A4 Inhibition) | In Vivo Studies Showed No Significant Effects on Indinavir Exposure | No dosage adjustment for indinavir when coadministered with Voriconazole for injection
Other HIV Protease Inhibitors (CYP3A4 Inhibition) | In Vitro Studies Demonstrated Potential for Voriconazole to Inhibit Metabolism (Increased Plasma Exposure) | Frequent monitoring for adverse reactions and toxicity related to other HIV protease inhibitors
Other NNRTIs [Non-Nucleoside Reverse Transcriptase Inhibitors] (CYP3A4 Inhibition) | A Voriconazole-Efavirenz Drug Interaction Study Demonstrated the Potential for Voriconazole to Inhibit Metabolism of Other NNRTIs (Increased Plasma Exposure) | Frequent monitoring for adverse reactions and toxicity related to NNRTI.
Tretinoin (CYP3A4 Inhibition) | Although Not Studied, Voriconazole may Increase Tretinoin Concentrations and Increase the Risk of Adverse Reactions | Frequent monitoring for signs and symptoms of pseudotumor cerebri or hypercalcemia.
Midazolam (CYP3A4 Inhibition) | Significantly Increased | Increased plasma exposures may increase the risk of adverse reactions and toxicities related to benzodiazepines.
Other benzodiazepines including triazolam and alprazolam (CYP3A4 Inhibition) | In Vitro Studies Demonstrated Potential for Voriconazole to Inhibit Metabolism (Increased Plasma Exposure) | Refer to drug-specific labeling for details.
HMG-CoA Reductase Inhibitors (Statins) (CYP3A4 Inhibition) | In Vitro Studies Demonstrated Potential for Voriconazole to Inhibit Metabolism (Increased Plasma Exposure) | Frequent monitoring for adverse reactions and toxicity related to statins. Increased statin concentrations in plasma have been associated with rhabdomyolysis. Adjustment of the statin dosage may be needed.
Dihydropyridine Calcium Channel Blockers (CYP3A4 Inhibition) | In Vitro Studies Demonstrated Potential for Voriconazole to Inhibit Metabolism (Increased Plasma Exposure) | Frequent monitoring for adverse reactions and toxicity related to calcium channel blockers. Adjustment of calcium channel blocker dosage may be needed.
Sulfonylurea Oral Hypoglycemics (CYP2C9 Inhibition) | Not Studied In Vivo or In Vitro, but Drug Plasma Exposure Likely to be Increased | Frequent monitoring of blood glucose and for signs and symptoms of hypoglycemia. Adjustment of oral hypoglycemic drug dosage may be needed.
Vinca Alkaloids (CYP3A4 Inhibition) | Not Studied In Vivo or In Vitro, but Drug Plasma Exposure Likely to be Increased | Frequent monitoring for adverse reactions and toxicity (i.e., neurotoxicity) related to vinca alkaloids. Reserve azole antifungals, including Voriconazole for injection, for patients receiving a vinca alkaloid who have no alternative antifungal treatment options.
Everolimus (CYP3A4 Inhibition) | Not Studied In Vivo or In Vitro, but Drug Plasma Exposure Likely to be Increased | Concomitant administration of Voriconazole for injection and everolimus is not recommended.

8 USE IN SPECIFIC POPULATIONS

8.1 Pregnancy

Risk Summary

Voriconazole can cause fetal harm when administered to a pregnant woman. There are no available data on the use of Voriconazole for injection in pregnant women. In animal reproduction studies, oral voriconazole was associated with fetal malformations in rats and fetal toxicity in rabbits. Cleft palates and hydronephrosis/hydroureter were observed in rat pups exposed to voriconazole during organogenesis at and above 10 mg/kg (0.3 times the RMD of 200 mg every 12 hours based on body surface area comparisons). In rabbits, embryomortality, reduced fetal weight and increased incidence of skeletal variations, cervical ribs and extrasternal ossification sites were observed in pups when pregnant rabbits were orally dosed at 100 mg/kg (6 times the RMD based on body surface area comparisons) during organogenesis. Rats exposed to voriconazole from implantation to weaning experienced increased gestational length and dystocia, which were associated with increased perinatal pup mortality at the 10 mg/kg dose [see Data]. If this drug is used during pregnancy, or if the patient becomes pregnant while taking this drug, inform the patient of the potential hazard to the fetus [see Warnings and Precautions (5.9)].

The background risk of major birth defects and miscarriage for the indicated populations is unknown. In the U.S. general population, the estimated background risk of major birth defects and miscarriage in clinically recognized pregnancies is 2-4% and 15-20% respectively.

Data

Animal Data

Voriconazole was administered orally to pregnant rats during organogenesis (gestation days 6-17) at 10, 30, and 60 mg/kg/day. Voriconazole was associated with increased incidences of the malformations in hydroureter and hydronephrosis at 10 mg/kg/day or greater, approximately 0.3 times the recommended human dose (RMD) based on body surface area comparisons, and cleft palate at 60 mg/kg, approximately 2 times the RMD based on body surface area comparisons. Reduced ossification of sacral and caudal vertebrae, skull, pubic, and hyoid bone, supernumerary ribs, anomalies of the sternebrae, and dilatation of the ureter/renal pelvis were also observed at doses of 10 mg/kg or greater. There was no evidence of maternal toxicity at any dose.

Voriconazole was administered orally to pregnant rabbits during the period of organogenesis (gestation days 7-19) at 10, 40, and 100 mg/kg/day. Voriconazole was associated with increased post-implantation loss and decreased fetal body weight, in association with maternal toxicity (decreased body weight gain and food consumption) at 100 mg/kg/day (6 times the RMD based on body surface area comparisons). Fetal skeletal variations (increases in the incidence of cervical rib and extra sternebral ossification sites) were observed at 100 mg/kg/day.

In a peri- and postnatal toxicity study in rats, voriconazole was administered orally to female rats from implantation through the end of lactation at 1, 3, and 10 mg/kg/day. Voriconazole prolonged the duration of gestation and labor and produced dystocia with related increases in maternal mortality and decreases in perinatal survival of F1 pups at 10 mg/kg/day, approximately 0.3 times the RMD.

8.2 Lactation

Risk Summary

No data are available regarding the presence of voriconazole in human milk, the effects of voriconazole on the breastfed infant, or the effects on milk production. The developmental and health benefits of breastfeeding should be considered along with the mother's clinical need for Voriconazole for injection and any potential adverse effects on the breastfed child from Voriconazole for injection or from the underlying maternal condition.

8.3 Females and Males of Reproductive Potential

Contraception

Advise females of reproductive potential to use effective contraception during treatment with Voriconazole for injection. The coadministration of voriconazole with the oral contraceptive, Ortho-Novum® (35 mcg ethinyl estradiol and 1 mg norethindrone), results in an interaction between these two drugs, but is unlikely to reduce the contraceptive effect. Monitoring for adverse reactions associated with oral contraceptives and voriconazole is recommended [see Drug Interactions (7) and Clinical Pharmacology (12.3)].

8.4 Pediatric Use

The safety and effectiveness of voriconazole have been established in pediatric patients aged 12 to 14 years weighing greater than or equal to 50 kg and those aged 15 years and older regardless of body weight based on evidence from adequate and well-controlled studies in adult and pediatric patients and additional pediatric pharmacokinetic and safety data. A total of 51 pediatric patients aged 12 to less than 18 [N=51] from eight adult therapeutic trials provided safety information for voriconazole use in the pediatric population [see Adverse Reactions (6.1), Clinical Pharmacology (12.3), and Clinical Studies (14)].

Safety and effectiveness in pediatric patients below the age of 2 years has not been established. Therefore, Voriconazole for injection is not recommended for pediatric patients less than 2 years of age.

A higher frequency of liver enzyme elevations was observed in the pediatric patients [see Dosage and Administration (2.5), Warnings and Precautions (5.1), and Adverse Reactions (6.1)].

The frequency of phototoxicity reactions is higher in the pediatric population. Squamous cell carcinoma has been reported in patients who experience photosensitivity reactions. Stringent measures for photoprotection are warranted. Sun avoidance and dermatologic follow-up are recommended in pediatric patients experiencing photoaging injuries, such as lentigines or ephelides, even after treatment discontinuation [see Warnings and Precautions (5.6)].

Voriconazole for injection has not been studied in pediatric patients with hepatic or renal impairment [see Dosage and Administration (2.5, 2.6)]. Hepatic function and serum creatinine levels should be closely monitored in pediatric patients [see Dosage and Administration (2.6) and Warnings and Precautions (5.1, 5.10)].

Additional pediatric use information is approved for PF PRISM C.V.'s VFEND (voriconazole) for injection. However, due to PF PRISM C.V.'s marketing exclusivity rights, this drug product is not labeled with that information.

8.5 Geriatric Use

In multiple dose therapeutic trials of voriconazole, 9.2% of patients were ≥ 65 years of age and 1.8% of patients were ≥ 75 years of age. In a study in healthy subjects, the systemic exposure (AUC) and peak plasma concentrations (Cmax) were increased in elderly males compared to young males. Pharmacokinetic data obtained from 552 patients from 10 voriconazole therapeutic trials showed that voriconazole plasma concentrations in the elderly patients were approximately 80% to 90% higher than those in younger patients after either IV or oral administration. However, the overall safety profile of the elderly patients was similar to that of the young so no dosage adjustment is recommended [see Clinical Pharmacology (12.3)].

10 OVERDOSAGE

In clinical trials, there were three cases of accidental overdose. All occurred in pediatric patients who received up to five times the recommended intravenous dose of voriconazole. A single adverse event of photophobia of 10 minutes duration was reported.

There is no known antidote to voriconazole.

Voriconazole is hemodialyzed with clearance of 121 mL/min. The intravenous vehicle, HPβCD, is hemodialyzed with clearance of 37.5±24 mL/min. In an overdose, hemodialysis may assist in the removal of voriconazole and HPβCD from the body.

11 DESCRIPTION

Voriconazole for injection, an azole antifungal is available as a sterile lyophilized cake or powder for solution for intravenous infusion. The structural formula is:

Voriconazole is designated chemically as (2R,3S)-2-(2, 4-difluorophenyl)-3-(5-fluoro-4-pyrimidinyl)-1-(1H-1,2,4-triazol-1-yl)-2-butanol with an empirical formula of C16H14F3N5O and a molecular weight of 349.3.

Voriconazole drug substance is a white or almost white powder.

Voriconazole for injection is a white to off white lyophilized cake or powder containing nominally 200 mg voriconazole and 3200 mg hydroxypropyl β-cyclodextrin (HPβCD) in a 30 mL Type I clear glass vial.

Voriconazole for injection is intended for administration by intravenous infusion. It is an unpreserved product in a single dose vial. Vials containing 200 mg lyophilized voriconazole are intended for reconstitution with Water for Injection to produce a solution containing 10 mg/mL Voriconazole for injection and 160 mg/mL of hydroxypropyl β-cyclodextrin (HPβCD). The resultant solution is further diluted prior to administration as an intravenous infusion [see Dosage and Administration (2)].

12 CLINICAL PHARMACOLOGY

12.1 Mechanism of Action

Voriconazole is an antifungal drug [see Microbiology (12.4)].

12.2 Pharmacodynamics

Exposure-Response Relationship For Efficacy and Safety

In 10 clinical trials (N=1121), the median values for the average and maximum voriconazole plasma concentrations in individual patients across these studies was 2.51 µg/mL (inter-quartile range 1.21 to 4.44 µg/mL) and 3.79 µg/mL (inter-quartile range 2.06 to 6.31 µg/mL), respectively. A pharmacokinetic-pharmacodynamic analysis of patient data from 6 of these 10 clinical trials (N=280) could not detect a positive association between mean, maximum or minimum plasma voriconazole concentration and efficacy. However, pharmacokinetic/pharmacodynamic analyses of the data from all 10 clinical trials identified positive associations between plasma voriconazole concentrations and rate of both liver function test abnormalities and visual disturbances [see Adverse Reactions (6)].

Cardiac Electrophysiology

A placebo-controlled, randomized, crossover study to evaluate the effect on the QT interval of healthy male and female subjects was conducted with three single oral doses of voriconazole and ketoconazole. Serial ECGs and plasma samples were obtained at specified intervals over a 24-hour post dose observation period. The placebo-adjusted mean maximum increases in QTc from baseline after 800, 1200, and 1600 mg of voriconazole and after ketoconazole 800 mg were all <10 msec. Females exhibited a greater increase in QTc than males, although all mean changes were <10 msec. Age was not found to affect the magnitude of increase in QTc. No subject in any group had an increase in QTc of ≥60 msec from baseline. No subject experienced an interval exceeding the potentially clinically relevant threshold of 500 msec. However, the QT effect of voriconazole combined with drugs known to prolong the QT interval is unknown [see Contraindications (4) and Drug Interactions (7)].

12.3 Pharmacokinetics

The pharmacokinetics of voriconazole have been characterized in healthy subjects, special populations and patients.

The pharmacokinetics of voriconazole are non-linear due to saturation of its metabolism. The interindividual variability of voriconazole pharmacokinetics is high. Greater than proportional increase in exposure is observed with increasing dose. It is estimated that, on average, increasing the intravenous dose from 3 mg/kg every 12 hours to 4 mg/kg every 12 hours produces an approximately 2.5-fold increase in exposure (Table 8).

Table 8: Geometric Mean (%CV) Plasma Voriconazole Pharmacokinetic Parameters in Adults Receiving Different Dosing Regimens
 | 6 mg/kg IV (loading dose) | 3 mg/kg IV every 12 hours | 4 mg/kg IV every 12 hours
N | 35 | 23 | 40
AUC12 (μg∙h/mL) | 13.9 (32) | 13.7 (53) | 33.9 (54)
Cmax (μg/mL) | 3.13 (20) | 3.03 (25) | 4.77 (36)
Cmin (μg/mL) | -- | 0.46 (97) | 1.73 (74)
Note: Parameters were estimated based on non-compartmental analysis from 5 pharmacokinetic studies.
AUC12 = area under the curve over 12 hour dosing interval, Cmax = maximum plasma concentration, Cmin = minimum plasma concentration. CV = coefficient of variation.

When the recommended intravenous loading dose regimen is administered to healthy subjects, plasma concentrations close to steady state are achieved within the first 24 hours of dosing (e.g., 6 mg/kg IV every 12 hours on day 1 followed by 3 mg/kg IV every 12 hours). Without the loading dose, accumulation occurs during twice daily multiple dosing with steady state plasma voriconazole concentrations being achieved by day 6 in the majority of subjects.

Distribution

The volume of distribution at steady state for voriconazole is estimated to be 4.6 L/kg, suggesting extensive distribution into tissues. Plasma protein binding is estimated to be 58% and was shown to be independent of plasma concentrations (approximate range: 0.9–15 µg/mL). Varying degrees of hepatic and renal impairment do not affect the protein binding of voriconazole.

Elimination

Metabolism

In vitro studies showed that voriconazole is metabolized by the human hepatic cytochrome P450 enzymes, CYP2C19, CYP2C9 and CYP3A4 [see Drug Interactions (7)].

In vivo studies indicated that CYP2C19 is significantly involved in the metabolism of voriconazole. This enzyme exhibits genetic polymorphism [see Clinical Pharmacology (12.5)].

The major metabolite of voriconazole is the N-oxide, which accounts for 72% of the circulating radiolabelled metabolites in plasma. Since this metabolite has minimal antifungal activity, it does not contribute to the overall efficacy of voriconazole.

Excretion

Voriconazole is eliminated via hepatic metabolism with less than 2% of the dose excreted unchanged in the urine. After administration of a single radiolabelled dose of IV voriconazole, preceded by multiple IV dosing, approximately 80% to 83% of the radioactivity is recovered in the urine. The majority (>94%) of the total radioactivity is excreted in the first 96 hours after intravenous dosing.

As a result of non-linear pharmacokinetics, the terminal half-life of voriconazole is dose dependent and therefore not useful in predicting the accumulation or elimination of voriconazole.

Specific Populations

Male and Female Patients

In a multiple oral dose study, the mean Cmax and AUCτ for healthy young females were 83% and 113% higher, respectively, than in healthy young males (18–45 years), after tablet dosing. In the same study, no significant differences in the mean Cmax and AUCτ were observed between healthy elderly males and healthy elderly females (>65 years). In a similar study, after dosing with the oral suspension, the mean AUC for healthy young females was 45% higher than in healthy young males whereas the mean Cmax was comparable between genders. The steady state trough voriconazole concentrations (Cmin) seen in females were 100% and 91% higher than in males receiving the tablet and the oral suspension, respectively.

In the clinical program, no dosage adjustment was made on the basis of gender. The safety profile and plasma concentrations observed in male and female subjects were similar. Therefore, no dosage adjustment based on gender is necessary.

Geriatric Patients

In an oral multiple dose study the mean Cmax and AUCτ in healthy elderly males (≥ 65 years) were 61% and 86% higher, respectively, than in young males (18–45 years). No significant differences in the mean Cmax and AUCτ were observed between healthy elderly females (≥ 65 years) and healthy young females (18–45 years).

In the clinical program, no dosage adjustment was made on the basis of age. An analysis of pharmacokinetic data obtained from 552 patients from 10 voriconazole clinical trials showed that the median voriconazole plasma concentrations in the elderly patients (>65 years) were approximately 80% to 90% higher than those in the younger patients (≤65 years) after either IV or oral administration. However, the safety profile of voriconazole in young and elderly subjects was similar and, therefore, no dosage adjustment is necessary for the elderly [see Use in Specific Populations (8.5)].

Pediatric Patients

Voriconazole exposures in the majority of pediatric patients aged 12 to less than 17 years were comparable to those in adults receiving the same dosing regimens. However, lower voriconazole exposure was observed in some pediatric patients aged 12 to less than 17 years with low body weight compared to adults [see Dosage and Administration (2.4)].

Additional pediatric use information is approved for PF PRISM C.V.'s VFEND (voriconazole) for injection. However, due to PF PRISM C.V.'s marketing exclusivity rights, this drug product is not labeled with that information.

Patients with Hepatic Impairment

After a single oral dose (200 mg) of voriconazole in 8 patients with mild (Child-Pugh Class A) and 4 patients with moderate (Child-Pugh Class B) hepatic impairment, the mean systemic exposure (AUC) was 3.2-fold higher than in age and weight matched controls with normal hepatic function. There was no difference in mean peak plasma concentrations (Cmax) between the groups. When only the patients with mild (Child-Pugh Class A) hepatic impairment were compared to controls, there was still a 2.3-fold increase in the mean AUC in the group with hepatic impairment compared to controls.

In an oral multiple dose study, AUCτ was similar in 6 subjects with moderate hepatic impairment (Child-Pugh Class B) given a lower maintenance dose of 100 mg twice daily compared to 6 subjects with normal hepatic function given the standard 200 mg twice daily maintenance dose. The mean peak plasma concentrations (Cmax) were 20% lower in the hepatically impaired group.

No pharmacokinetic data are available for patients with severe hepatic cirrhosis (Child-Pugh Class C) [see Dosage and Administration (2.5)].

Patients with Renal Impairment

In a multiple dose study of IV voriconazole (6 mg/kg IV loading dose × 2, then 3 mg/kg IV × 5.5 days) in 7 patients with moderate renal impairment (creatinine clearance 30–50 mL/min), the systemic exposure (AUC) and peak plasma concentrations (Cmax) were not significantly different from those in 6 subjects with normal renal function.

However, in patients with moderate renal dysfunction, the pharmacokinetic profile of hydroxypropyl β-cyclodextrin (HPβCD), an ingredient of Voriconazole for injection, has a short half-life of 1 to 2 hours, and demonstrates no accumulation following successive daily doses. In healthy subjects and in patients with mild to severe renal insufficiency, the majority (>85 %) of an 8 g dose of HPβCD is eliminated in the urine. In a study investigating another antifungal drug, itraconazole, following a single intravenous 200 mg dose, clearance of hydroxypropyl-β-cyclodextrin was reduced in subjects with renal impairment, resulting in higher exposure to hydroxypropyl-β-cyclodextrin. In subjects with mild, moderate, and severe renal impairment, half-life values were increased over normal values by approximately two-, four-, and six-fold, respectively. In these patients, successive infusions may result in accumulation of HPβCD until steady state is reached. HPβCD is hemodialyzed with a clearance of 37.5±24 mL/min.

A pharmacokinetic study in subjects with renal failure undergoing hemodialysis showed that voriconazole is dialyzed with clearance of 121 mL/min. A 4-hour hemodialysis session does not remove a sufficient amount of voriconazole to warrant dose adjustment [see Dosage and Administration (2.6)].

Patients at Risk of Aspergillosis

The observed voriconazole pharmacokinetics in patients at risk of aspergillosis (mainly patients with malignant neoplasms of lymphatic or hematopoietic tissue) were similar to healthy subjects.

Drug Interaction Studies

Effects of Other Drugs on Voriconazole

Voriconazole is metabolized by the human hepatic cytochrome P450 enzymes CYP2C19, CYP2C9, and CYP3A4. Results of in vitro metabolism studies indicate that the affinity of voriconazole is highest for CYP2C19, followed by CYP2C9, and is appreciably lower for CYP3A4. Inhibitors or inducers of these three enzymes may increase or decrease voriconazole systemic exposure (plasma concentrations), respectively.

The systemic exposure to voriconazole is significantly reduced by the concomitant administration of the following agents and their use is contraindicated:

Rifampin (potent CYP450 inducer)–Rifampin (600 mg once daily) decreased the steady state Cmax and AUCτ of voriconazole (200 mg every 12 hours × 7 days) by an average of 93% and 96%, respectively, in healthy subjects. Doubling the dose of voriconazole to 400 mg every 12 hours does not restore adequate exposure to voriconazole during coadministration with rifampin [see Contraindications (4)].

Ritonavir (potent CYP450 inducer; CYP3A4 inhibitor and substrate)–The effect of the coadministration of voriconazole and ritonavir (400 mg and 100 mg) was investigated in two separate studies. High-dose ritonavir (400 mg every 12 hours for 9 days) decreased the steady state Cmax and AUCτ of oral voriconazole (400 mg every 12 hours for 1 day, then 200 mg every 12 hours for 8 days) by an average of 66% and 82%, respectively, in healthy subjects. Low-dose ritonavir (100 mg every 12 hours for 9 days) decreased the steady state Cmax and AUCτ of oral voriconazole (400 mg every 12 hours for 1 day, then 200 mg every 12 hours for 8 days) by an average of 24% and 39%, respectively, in healthy subjects. Although repeat oral administration of voriconazole did not have a significant effect on steady state Cmax and AUCτ of high-dose ritonavir in healthy subjects, steady state Cmax and AUCτ of low-dose ritonavir decreased slightly by 24% and 14% respectively, when administered concomitantly with oral voriconazole in healthy subjects [see Contraindications (4)].

St. John's Wort (CYP450 inducer; P-gp inducer)–In an independent published study in healthy volunteers who were given multiple oral doses of St. John's Wort (300 mg LI 160 extract three times daily for 15 days) followed by a single 400 mg oral dose of voriconazole, a 59% decrease in mean voriconazole AUC0–∞ was observed. In contrast, coadministration of single oral doses of St. John's Wort and voriconazole had no appreciable effect on voriconazole AUC0–∞. Long-term use of St. John's Wort could lead to reduced voriconazole exposure [see Contraindications (4)].

Significant drug interactions that may require voriconazole dosage adjustment, or frequent monitoring of voriconazole-related adverse reactions/toxicity:

Fluconazole (CYP2C9, CYP2C19 and CYP3A4 inhibitor): Concurrent administration of oral voriconazole (400 mg every 12 hours for 1 day, then 200 mg every 12 hours for 2.5 days) and oral fluconazole (400 mg on day 1, then 200 mg every 24 hours for 4 days) to 6 healthy male subjects resulted in an increase in Cmax and AUCτ of voriconazole by an average of 57% (90% CI: 20%, 107%) and 79% (90% CI: 40%, 128%), respectively. In a follow-on clinical study involving 8 healthy male subjects, reduced dosing and/or frequency of voriconazole and fluconazole did not eliminate or diminish this effect [see Drug Interactions (7)].

Letermovir (CYP2C9/2C19 inducer)–Coadministration of oral letermovir with oral voriconazole decreased the steady state Cmax and AUC0-12 of voriconazole by an average of 39% and 44%, respectively [see Drug Interactions (7)].

Minor or no significant pharmacokinetic interactions that do not require dosage adjustment:

Cimetidine (non-specific CYP450 inhibitor and increases gastric pH)–Cimetidine (400 mg every 12 hours × 8 days) increased voriconazole steady state Cmax and AUCτ by an average of 18% (90% CI: 6%, 32%) and 23% (90% CI: 13%, 33%), respectively, following oral doses of 200 mg every 12 hours × 7 days to healthy subjects.

Ranitidine (increases gastric pH)–Ranitidine (150 mg every 12 hours) had no significant effect on voriconazole Cmax and AUCτ following oral doses of 200 mg every 12 hours × 7 days to healthy subjects.

Macrolide antibiotics–Coadministration of erythromycin (CYP3A4 inhibitor; 1gram every 12 hours for 7 days) or azithromycin (500 mg every 24 hours for 3 days) with voriconazole 200 mg every 12 hours for 14 days had no significant effect on voriconazole steady state Cmax and AUCτ in healthy subjects. The effects of voriconazole on the pharmacokinetics of either erythromycin or azithromycin are not known.

Effects of Voriconazole on Other Drugs

In vitro studies with human hepatic microsomes show that voriconazole inhibits the metabolic activity of the cytochrome P450 enzymes CYP2C19, CYP2C9, and CYP3A4. In these studies, the inhibition potency of voriconazole for CYP3A4 metabolic activity was significantly less than that of two other azoles, ketoconazole and itraconazole. In vitro studies also show that the major metabolite of voriconazole, voriconazole N-oxide, inhibits the metabolic activity of CYP2C9 and CYP3A4 to a greater extent than that of CYP2C19. Therefore, there is potential for voriconazole and its major metabolite to increase the systemic exposure (plasma concentrations) of other drugs metabolized by these CYP450 enzymes.

The systemic exposure of the following drugs is significantly increased by coadministration of voriconazole and their use is contraindicated:

Sirolimus (CYP3A4 substrate)–Repeat dose administration of oral voriconazole (400 mg every 12 hours for 1 day, then 200 mg every 12 hours for 8 days) increased the Cmax and AUC of sirolimus (2 mg single dose) an average of 7-fold (90% CI: 5.7, 7.5) and 11-fold (90% CI: 9.9, 12.6), respectively, in healthy male subjects [see Contraindications (4)].

Coadministration of voriconazole with the following agents results in increased exposure to these drugs. Therefore, careful monitoring and/or dosage adjustment of these drugs is needed:

Alfentanil (CYP3A4 substrate)–Coadministration of multiple doses of oral voriconazole (400 mg every 12 hours on day 1, 200 mg every 12 hours on day 2) with a single 20 mcg/kg intravenous dose of alfentanil with concomitant naloxone resulted in a 6-fold increase in mean alfentanil AUC0–∞ and a 4-fold prolongation of mean alfentanil elimination half-life, compared to when alfentanil was given alone [see Drug Interactions (7)].

Fentanyl (CYP3A4 substrate): In an independent published study, concomitant use of voriconazole (400 mg every 12 hours on Day 1, then 200 mg every 12 hours on Day 2) with a single intravenous dose of fentanyl (5 µg/kg) resulted in an increase in the mean AUC0–∞ of fentanyl by 1.4-fold (range 0.81- to 2.04-fold) [see Drug Interactions (7)].

Oxycodone (CYP3A4 substrate): In an independent published study, coadministration of multiple doses of oral voriconazole (400 mg every 12 hours, on Day 1 followed by five doses of 200 mg every 12 hours on Days 2 to 4) with a single 10 mg oral dose of oxycodone on Day 3 resulted in an increase in the mean Cmax and AUC0–∞ of oxycodone by 1.7-fold (range 1.4- to 2.2-fold) and 3.6-fold (range 2.7- to 5.6-fold), respectively. The mean elimination half-life of oxycodone was also increased by 2.0-fold (range 1.4- to 2.5-fold) [see Drug Interactions (7)].

Cyclosporine (CYP3A4 substrate)–In stable renal transplant recipients receiving chronic cyclosporine therapy, concomitant administration of oral voriconazole (200 mg every 12 hours for 8 days) increased cyclosporine Cmax and AUCτ an average of 1.1 times (90% CI: 0.9, 1.41) and 1.7 times (90% CI: 1.5, 2.0), respectively, as compared to when cyclosporine was administered without voriconazole [see Drug Interactions (7)].

Methadone (CYP3A4, CYP2C19, CYP2C9 substrate)–Repeat dose administration of oral voriconazole (400 mg every 12 hours for 1 day, then 200 mg every 12 hours for 4 days) increased the Cmax and AUCτ of pharmacologically active Rmethadone by 31% (90% CI: 22%, 40%) and 47% (90% CI: 38%, 57%), respectively, in subjects receiving a methadone maintenance dose (30–100 mg every 24 hours). The Cmax and AUC of (S)-methadone increased by 65% (90% CI: 53%, 79%) and 103% (90% CI: 85%, 124%), respectively [see Drug Interactions (7)].

Tacrolimus (CYP3A4 substrate)–Repeat oral dose administration of voriconazole (400 mg every 12 hours × 1 day, then 200 mg every 12 hours × 6 days) increased tacrolimus (0.1 mg/kg single dose) Cmax and AUCτ in healthy subjects by an average of 2-fold (90% CI: 1.9, 2.5) and 3-fold (90% CI: 2.7, 3.8), respectively [see Drug Interactions (7)].

Warfarin (CYP2C9 substrate)–Coadministration of voriconazole (300 mg every 12 hours × 12 days) with warfarin (30 mg single dose) significantly increased maximum prothrombin time by approximately 2 times that of placebo in healthy subjects [see Drug Interactions (7)].

Non-Steroidal Anti-Inflammatory Drugs (NSAIDs; CYP2C9 substrates): In two independent published studies, single doses of ibuprofen (400 mg) and diclofenac (50 mg) were coadministered with the last dose of voriconazole (400 mg every 12 hours on Day 1, followed by 200 mg every 12 hours on Day 2). Voriconazole increased the mean Cmax and AUC of the pharmacologically active isomer, S (+)-ibuprofen by 20% and 100%, respectively. Voriconazole increased the mean Cmax and AUC of diclofenac by 114% and 78%, respectively [see Drug Interactions (7)].

No significant pharmacokinetic interactions were observed when voriconazole was coadministered with the following agents. Therefore, no dosage adjustment for these agents is recommended:

Prednisolone (CYP3A4 substrate)–Voriconazole (200 mg every 12 hours × 30 days) increased Cmax and AUC of prednisolone (60 mg single dose) by an average of 11% and 34%, respectively, in healthy subjects [see Warnings and Precautions (5.8)].

Digoxin (P-glycoprotein mediated transport)–Voriconazole (200 mg every 12 hours × 12 days) had no significant effect on steady state Cmax and AUCτ of digoxin (0.25 mg once daily for 10 days) in healthy subjects.

Mycophenolic acid (UDP-glucuronyl transferase substrate)–Voriconazole (200 mg every 12 hours × 5 days) had no significant effect on the Cmax and AUCτ of mycophenolic acid and its major metabolite, mycophenolic acid glucuronide after administration of a 1gram single oral dose of mycophenolate mofetil.

Two-Way Interactions

Concomitant use of the following agents with voriconazole is contraindicated:

Rifabutin (potent CYP450 inducer)–Rifabutin (300 mg once daily) decreased the Cmax and AUCτ of voriconazole at 200 mg twice daily by an average of 67% (90% CI: 58%, 73%) and 79% (90% CI: 71%, 84%), respectively, in healthy subjects. During coadministration with rifabutin (300 mg once daily), the steady state Cmax and AUCτ of voriconazole following an increased dose of 400 mg twice daily were on average approximately 2 times higher, compared with voriconazole alone at 200 mg twice daily. Coadministration of voriconazole at 400 mg twice daily with rifabutin 300 mg twice daily increased the Cmax and AUCτ of rifabutin by an average of 3-times (90% CI: 2.2, 4.0) and 4 times (90% CI: 3.5, 5.4), respectively, compared to rifabutin given alone [see Contraindications (4)].

Significant drug interactions that may require dosage adjustment, frequent monitoring of drug levels and/or frequent monitoring of drug-related adverse reactions/toxicity:

Efavirenz, a non-nucleoside reverse transcriptase inhibitor (CYP450 inducer; CYP3A4 inhibitor and substrate)–Standard doses of voriconazole and efavirenz (400 mg every 24 hours or higher) must not be coadministered [see Drug Interactions (7)]. Steady state efavirenz (400 mg PO every 24 hours) decreased the steady state Cmax and AUCτ of voriconazole (400 mg PO every 12 hours for 1 day, then 200 mg PO every 12 hours for 8 days) by an average of 61% and 77%, respectively, in healthy male subjects. Voriconazole at steady state (400 mg PO every 12 hours for 1 day, then 200 mg every 12 hours for 8 days) increased the steady state Cmax and AUCτ of efavirenz (400 mg PO every 24 hours for 9 days) by an average of 38% and 44%, respectively, in healthy subjects.

Phenytoin (CYP2C9 substrate and potent CYP450 inducer)–Repeat dose administration of phenytoin (300 mg once daily) decreased the steady state Cmax and AUCτ of orally administered voriconazole (200 mg every 12 hours × 14 days) by an average of 50% and 70%, respectively, in healthy subjects. Administration of a higher voriconazole dose (400 mg every 12 hours × 7 days) with phenytoin (300 mg once daily) resulted in comparable steady state voriconazole Cmax and AUCτ estimates as compared to when voriconazole was given at 200 mg every 12 hours without phenytoin [see Dosage and Administration (2.7) and Drug Interactions (7)].

Repeat dose administration of voriconazole (400 mg every 12 hours × 10 days) increased the steady state Cmax and AUCτ of phenytoin (300 mg once daily) by an average of 70% and 80%, respectively, in healthy subjects. The increase in phenytoin Cmax and AUC when coadministered with voriconazole may be expected to be as high as 2 times the Cmax and AUC estimates when phenytoin is given without voriconazole. Therefore, frequent monitoring of plasma phenytoin concentrations and phenytoin-related adverse effects is recommended when phenytoin is coadministered with voriconazole [see Drug Interactions (7)].

Omeprazole (CYP2C19 inhibitor; CYP2C19 and CYP3A4 substrate)–Coadministration of omeprazole (40 mg once daily × 10 days) with oral voriconazole (400 mg every 12 hours × 1 day, then 200 mg every 12 hours × 9 days) increased the steady state Cmax and AUCτ of voriconazole by an average of 15% (90% CI: 5%, 25%) and 40% (90% CI: 29%, 55%), respectively, in healthy subjects. No dosage adjustment of voriconazole is recommended.

Coadministration of voriconazole (400 mg every 12 hours × 1 day, then 200 mg × 6 days) with omeprazole (40 mg once daily × 7 days) to healthy subjects significantly increased the steady state Cmax and AUCτ of omeprazole an average of 2 times (90% CI: 1.8, 2.6) and 4 times (90% CI: 3.3, 4.4), respectively, as compared to when omeprazole is given without voriconazole [see Drug Interactions (7)].

Oral Contraceptives (CYP3A4 substrate; CYP2C19 inhibitor)–Coadministration of oral voriconazole (400 mg every 12 hours for 1 day, then 200 mg every 12 hours for 3 days) and oral contraceptive (Ortho-Novum1/35® consisting of 35 mcg ethinyl estradiol and 1 mg norethindrone, every 24 hours) to healthy female subjects at steady state increased the Cmax and AUCτ of ethinyl estradiol by an average of 36% (90% CI: 28%, 45%) and 61% (90% CI: 50%, 72%), respectively, and that of norethindrone by 15% (90% CI: 3%, 28%) and 53% (90% CI: 44%, 63%), respectively in healthy subjects. Voriconazole Cmax and AUCτ increased by an average of 14% (90% CI: 3%, 27%) and 46% (90% CI: 32%, 61%), respectively [see Drug Interactions (7)].

No significant pharmacokinetic interaction was seen and no dosage adjustment of these drugs is recommended:

Indinavir (CYP3A4 inhibitor and substrate)–Repeat dose administration of indinavir (800 mg TID for 10 days) had no significant effect on voriconazole Cmax and AUC following repeat dose administration (200 mg every 12 hours for 17 days) in healthy subjects.

Repeat dose administration of voriconazole (200 mg every 12 hours for 7 days) did not have a significant effect on steady state Cmax and AUCτ of indinavir following repeat dose administration (800 mg TID for 7 days) in healthy subjects.

12.4 Microbiology

Mechanism of Action

Voriconazole is an azole antifungal drug. The primary mode of action of voriconazole is the inhibition of fungal cytochrome P-450-mediated 14 alpha-lanosterol demethylation, an essential step in fungal ergosterol biosynthesis. The accumulation of 14 alpha-methyl sterols correlates with the subsequent loss of ergosterol in the fungal cell wall and may be responsible for the antifungal activity of voriconazole.

Resistance

A potential for development of resistance to voriconazole is well known. The mechanisms of resistance may include mutations in the gene ERG11 (encodes for the target enzyme, lanosterol 14-α-demethylase), upregulation of genes encoding the ATP-binding cassette efflux transporters i.e., Candida drug resistance (CDR) pumps and reduced access of the drug to the target, or some combination of those mechanisms. The frequency of drug resistance development for the various fungi for which this drug is indicated is not known.

Fungal isolates exhibiting reduced susceptibility to fluconazole or itraconazole may also show reduced susceptibility to voriconazole, suggesting cross-resistance can occur among these azoles. The relevance of cross-resistance and clinical outcome has not been fully characterized. Clinical cases where azole cross-resistance is demonstrated may require alternative antifungal therapy.

Antimicrobial Activity

Voriconazole has been shown to be active against most isolates of the following microorganisms, both in vitro and in clinical infections.

Aspergillus fumigatus
Aspergillus flavus
Aspergillus niger
Aspergillus terreus
Candida albicans
Candida glabrata (In clinical studies, the voriconazole MIC90 was 4 µg/mL) [In clinical studies, voriconazole MIC90 for C. glabrata baseline isolates was 4 µg/mL; 13/50 (26%) C. glabrata baseline isolates were resistant (MIC ≥4 µg/mL) to voriconazole. However, based on 1054 isolates tested in surveillance studies the MIC90 was 1 µg/mL.]
Candida krusei
Candida parapsilosis
Candida tropicalis
Fusarium spp. including Fusarium solani
Scedosporium apiospermum

The following data are available, but their clinical significance is unknown. At least 90 percent of the following fungi exhibit an in vitro minimum inhibitory concentration (MIC) less than or equal to the susceptible breakpoint for voriconazole against isolates of similar genus or organism group. However, the effectiveness of voriconazole in treating clinical infections due to these fungi has not been established in adequate and well-controlled clinical trials:

Candida lusitaniae
Candida guilliermondii

Susceptibility Testing

For specific information regarding susceptibility test interpretive criteria and associated test methods and quality control standards recognized by FDA for this drug, please see: https://www.fda.gov/STIC.

12.5 Pharmacogenomics

CYP2C19, significantly involved in the metabolism of voriconazole, exhibits genetic polymorphism. Approximately 15-20% of Asian populations may be expected to be poor metabolizers. For Caucasians and Blacks, the prevalence of poor metabolizers is 3-5%. Studies conducted in Caucasian and Japanese healthy subjects have shown that poor metabolizers have, on average, 4-fold higher voriconazole exposure (AUCτ) than their homozygous extensive metabolizer counterparts. Subjects who are heterozygous extensive metabolizers have, on average, 2-fold higher voriconazole exposure than their homozygous extensive metabolizer counterparts [see Clinical Pharmacology (12.3)].

13 NONCLINICAL TOXICOLOGY

13.1 Carcinogenesis, Mutagenesis, Impairment of Fertility

Two-year carcinogenicity studies were conducted in rats and mice. Rats were given oral doses of 6, 18 or 50 mg/kg voriconazole, or 0.2, 0.6, or 1.6 times the RMD on a body surface area basis. Hepatocellular adenomas were detected in females at 50 mg/kg and hepatocellular carcinomas were found in males at 6 and 50 mg/kg. Mice were given oral doses of 10, 30 or 100 mg/kg voriconazole, or 0.1, 0.4, or 1.4 times the RMD on a body surface area basis. In mice, hepatocellular adenomas were detected in males and females and hepatocellular carcinomas were detected in males at 1.4 times the RMD of voriconazole.

Voriconazole demonstrated clastogenic activity (mostly chromosome breaks) in human lymphocyte cultures in vitro. Voriconazole was not genotoxic in the Ames assay, CHO HGPRT assay, the mouse micronucleus assay or the in vivo DNA repair test (Unscheduled DNA Synthesis assay).

Voriconazole administration induced no impairment of male or female fertility in rats dosed at 50 mg/kg, or 1.6 times the RMD.

14 CLINICAL STUDIES

Voriconazole, administered orally or parenterally, has been evaluated as primary or salvage therapy in 520 patients aged 12 years and older with infections caused by Aspergillus spp., Fusarium spp., and Scedosporium spp.

14.1 Invasive Aspergillosis (IA)

Voriconazole was studied in patients for primary therapy of IA (randomized, controlled study 307/602), for primary and salvage therapy of aspergillosis (non-comparative study 304) and for treatment of patients with IA who were refractory to, or intolerant of, other antifungal therapy (non-comparative study 309/604).

Study 307/602 – Primary Therapy of Invasive Aspergillosis

The efficacy of voriconazole compared to amphotericin B in the primary treatment of acute IA was demonstrated in 277 patients treated for 12 weeks in a randomized, controlled study (Study 307/602). The majority of study patients had underlying hematologic malignancies, including bone marrow transplantation. The study also included patients with solid organ transplantation, solid tumors, and AIDS. The patients were mainly treated for definite or probable IA of the lungs. Other aspergillosis infections included disseminated disease, CNS infections and sinus infections. Diagnosis of definite or probable IA was made according to criteria modified from those established by the National Institute of Allergy and Infectious Diseases Mycoses Study Group/European Organisation for Research and Treatment of Cancer (NIAID MSG/EORTC).

Voriconazole was administered intravenously with a loading dose of 6 mg/kg every 12 hours for the first 24 hours followed by a maintenance dose of 4 mg/kg every 12 hours for a minimum of 7 days. Therapy could then be switched to the oral formulation at a dose of 200 mg every 12 hours. Median duration of IV voriconazole therapy was 10 days (range 2–85 days). After IV voriconazole therapy, the median duration of PO voriconazole therapy was 76 days (range 2–232 days).

Patients in the comparator group received conventional amphotericin B as a slow infusion at a daily dose of 1.0–1.5 mg/kg/day. Median duration of IV amphotericin therapy was 12 days (range 1–85 days). Treatment was then continued with OLAT, including itraconazole and lipid amphotericin B formulations. Although initial therapy with conventional amphotericin B was to be continued for at least two weeks, actual duration of therapy was at the discretion of the investigator. Patients who discontinued initial randomized therapy due to toxicity or lack of efficacy were eligible to continue in the study with OLAT treatment.

A satisfactory global response at 12 weeks (complete or partial resolution of all attributable symptoms, signs, radiographic/bronchoscopic abnormalities present at baseline) was seen in 53% of voriconazole treated patients compared to 32% of amphotericin B treated patients (Table 11). A benefit of voriconazole compared to amphotericin B on patient survival at Day 84 was seen with a 71% survival rate on voriconazole compared to 58% on amphotericin B (Table 9).

Table 9 also summarizes the response (success) based on mycological confirmation and species.

Table 9: Overall Efficacy and Success by Species in the Primary Treatment of Acute Invasive Aspergillosis Study 307/602
 | Voriconazole | Ampho B [Amphotericin B followed by other licensed antifungal therapy] | Stratified Difference (95% CI) [Difference and corresponding 95% confidence interval are stratified by protocol]
 | n/N (%) | n/N (%)
Efficacy as Primary Therapy
Satisfactory Global Response [Assessed by independent Data Review Committee (DRC)] | 76/144 (53) | 42/133 (32) | 21.8% (10.5%, 33.0%) p<0.0001
Survival at Day 84 [Proportion of subjects alive] | 102/144 (71) | 77/133 (58) | 13.1% (2.1%, 24.2%)
Success by Species
 | Success n/N (%)
Overall success | 76/144 (53) | 42/133 (32)
Mycologically confirmed [Not all mycologically confirmed specimens were speciated] | 37/84 (44) | 16/67 (24)
Aspergillus spp. [Some patients had more than one species isolated at baseline]
A. fumigatus | 28/63 (44) | 12/47 (26)
A. flavus | 3/6 | 4/9
A. terreus | 2/3 | 0/3
A. niger | 1/4 | 0/9
A. nidulans | 1/1 | 0/0

Study 304 – Primary and Salvage Therapy of Aspergillosis

In this non-comparative study, an overall success rate of 52% (26/50) was seen in patients treated with voriconazole for primary therapy. Success was seen in 17/29 (59%) with Aspergillus fumigatus infections and 3/6 (50%) patients with infections due to non-fumigatus species [A. flavus (1/1); A. nidulans (0/2); A. niger (2/2); A. terreus (0/1)]. Success in patients who received voriconazole as salvage therapy is presented in Table 10.

Study 309/604 – Treatment of Patients with Invasive Aspergillosis who were Refractory to, or Intolerant of, other Antifungal Therapy

Additional data regarding response rates in patients who were refractory to, or intolerant of, other antifungal agents are also provided in Table 11. In this non-comparative study, overall mycological eradication for culture-documented infections due to fumigatus and non-fumigatus species of Aspergillus was 36/82 (44%) and 12/30 (40%), respectively, in voriconazole treated patients. Patients had various underlying diseases and species other than A. fumigatus contributed to mixed infections in some cases.

For patients who were infected with a single pathogen and were refractory to, or intolerant of, other antifungal agents, the satisfactory response rates for voriconazole in studies 304 and 309/604 are presented in Table 10.

Table 10: Combined Response Data in Salvage Patients with Single Aspergillus Species (Studies 304 and 309/604)
 | Success n/N
A. fumigatus | 43/97 (44%)
A. flavus | 5/12
A. nidulans | 1/3
A. niger | 4/5
A. terreus | 3/8
A. versicolor | 0/1

Nineteen patients had more than one species of Aspergillus isolated. Success was seen in 4/17 (24%) of these patients.

14.2 Candidemia in Non-neutropenic Patients and Other Deep Tissue Candida Infections

Voriconazole was compared to the regimen of amphotericin B followed by fluconazole in Study 608, an open-label, comparative study in nonneutropenic patients with candidemia associated with clinical signs of infection. Patients were randomized in 2:1 ratio to receive either voriconazole (n=283) or the regimen of amphotericin B followed by fluconazole (n=139). Patients were treated with randomized study drug for a median of 15 days. Most of the candidemia in patients evaluated for efficacy was caused by C. albicans (46%), followed by C. tropicalis (19%), C. parapsilosis (17%), C. glabrata (15%), and C. krusei (1%).

An independent Data Review Committee (DRC), blinded to study treatment, reviewed the clinical and mycological data from this study, and generated one assessment of response for each patient. A successful response required all of the following: resolution or improvement in all clinical signs and symptoms of infection, blood cultures negative for Candida, infected deep tissue sites negative for Candida or resolution of all local signs of infection, and no systemic antifungal therapy other than study drug. The primary analysis, which counted DRC-assessed successes at the fixed time point (12 weeks after End of Therapy [EOT]), demonstrated that voriconazole was comparable to the regimen of amphotericin B followed by fluconazole (response rates of 41% and 41%, respectively) in the treatment of candidemia. Patients who did not have a 12-week assessment for any reason were considered a treatment failure.

The overall clinical and mycological success rates by Candida species in Study 150-608 are presented in Table 11.

Table 11: Overall Success Rates Sustained From EOT To The Fixed 12-Week Follow-Up Time Point By Baseline Pathogen [A few patients had more than one pathogen at baseline.] , [Patients who did not have a 12-week assessment for any reason were considered a treatment failure.]
Baseline Pathogen | Clinical and Mycological Success (%)
 | Voriconazole | Amphotericin B --> Fluconazole
C. albicans | 46/107 (43%) | 30/63 (48%)
C. tropicalis | 17/53 (32%) | 1/16 (6%)
C. parapsilosis | 24/45 (53%) | 10/19 (53%)
C. glabrata | 12/36 (33%) | 7/21 (33%)
C. krusei | 1/4 | 0/1

In a secondary analysis, which counted DRC-assessed successes at any time point (EOT, or 2, 6, or 12 weeks after EOT), the response rates were 65% for voriconazole and 71% for the regimen of amphotericin B followed by fluconazole.

In Studies 608 and 309/604 (non-comparative study in patients with invasive fungal infections who were refractory to, or intolerant of, other antifungal agents), voriconazole was evaluated in 35 patients with deep tissue Candida infections. A favorable response was seen in 4 of 7 patients with intra-abdominal infections, 5 of 6 patients with kidney and bladder wall infections, 3 of 3 patients with deep tissue abscess or wound infection, 1 of 2 patients with pneumonia/pleural space infections, 2 of 4 patients with skin lesions, 1 of 1 patients with mixed intra-abdominal and pulmonary infection, 1 of 2 patients with suppurative phlebitis, 1 of 3 patients with hepatosplenic infection, 1 of 5 patients with osteomyelitis, 0 of 1 with liver infection, and 0 of 1 with cervical lymph node infection.

14.3 Other Serious Fungal Pathogens

In pooled analyses of patients, voriconazole was shown to be effective against the following additional fungal pathogens:

Scedosporium apiospermum - Successful response to voriconazole therapy was seen in 15 of 24 patients (63%). Three of these patients relapsed within 4 weeks, including 1 patient with pulmonary, skin and eye infections, 1 patient with cerebral disease, and 1 patient with skin infection. Ten patients had evidence of cerebral disease and 6 of these had a successful outcome (1 relapse). In addition, a successful response was seen in 1 of 3 patients with mixed organism infections.

Fusarium spp. - Nine of 21 (43%) patients were successfully treated with voriconazole. Of these 9 patients, 3 had eye infections, 1 had an eye and blood infection, 1 had a skin infection, 1 had a blood infection alone, 2 had sinus infections, and 1 had disseminated infection (pulmonary, skin, hepatosplenic). Three of these patients (1 with disseminated disease, 1 with an eye infection and 1 with a blood infection) had Fusarium solani and were complete successes. Two of these patients relapsed, 1 with a sinus infection and profound neutropenia and 1 post surgical patient with blood and eye infections.

14.4 Pediatric Studies

A total of 22 patients aged 12 to 18 years with IA were included in the adult therapeutic studies. Twelve out of 22 (55%) patients had successful response after treatment with a maintenance dose of voriconazole 4 mg/kg every 12 hours.

Additional pediatric use information is approved for PF PRISM C.V.'s VFEND (voriconazole) for injection. However, due to PF PRISM C.V.'s marketing exclusivity rights, this drug product is not labeled with that information.

16 HOW SUPPLIED/STORAGE AND HANDLING

16.1 How Supplied

Voriconazole for injection is supplied in a single dose-vial as a sterile white to off white lyophilized cake or powder equivalent to 200 mg voriconazole and 3,200 mg hydroxypropyl β-cyclodextrin (HPβCD). It does not contain preservatives and is not made with natural rubber latex.

Individually packaged vials of Voriconazole for injection, 200 mg, NDC 70594-067-01.

16.2 Storage

Powder for Injection: Voriconazole for injection unreconstituted vials should be stored at 20°C – 25°C (68°F – 77°F); excursions permitted between 15°C and 30°C (59°F and 86°F) [see USP Controlled Room Temperature].

Reconstituted Drug Solution: From a microbiological point of view, following reconstitution of the lyophile with Water for Injection, the reconstituted solution should be used immediately. If not used immediately, in-use storage times and conditions prior to use are the responsibility of the user and should not be longer than 24 hours at 2°C to 8°C (36° to 46°F). Chemical and physical in-use stability has been demonstrated for 24 hours at 2°C to 8°C (36° to 46°F). Discard Unused Portion [see Dosage and Administration (2.8)].

Further Diluted Drug Solution for Infusion: Once the reconstituted product is further diluted for infusion, it should be used immediately. Discard Unused Portion [see Dosage and Administration (2.8)].

This medicinal product is for single use only and any unused solution should be discarded. Only clear solutions without particles should be used [see Dosage and Administration (2.8)].

17 PATIENT COUNSELING INFORMATION

Visual Disturbances

Patients should be instructed that visual disturbances such as blurring and sensitivity to light may occur with the use of voriconazole.

Photosensitivity

- Advise patients of the risk of photosensitivity (with or without concomitant methotrexate), accelerated photoaging, and skin cancer.
- Advise patients that Voriconazole for injection can cause serious photosensitivity and to immediately contact their healthcare provider for new or worsening skin rash.
- Advise patients to avoid exposure to direct sun light and to use measures such as protective clothing and sunscreen with high sun protection factor (SPF).

Embryo-Fetal Toxicity

- Advise female patients of the potential risks to a fetus.
- Advise females of reproductive potential to use effective contraception during treatment with Voriconazole for injection.

Manufactured for:

Xellia Pharmaceuticals USA, LLC
Buffalo Grove, IL 60089
United States of America

Made in India

1313000874-00

PRINCIPAL DISPLAY PANEL - 200 MG Vial Label

NDC 70594-067-01
Rx Only

Voriconazole
for Injection

200 MG* per vial

Not made with natural rubber latex
No Preservatives

Sterile Single Dose Vial
Must be reconstituted then diluted
For Intravenous Infusion Only
Discard Unused Portion